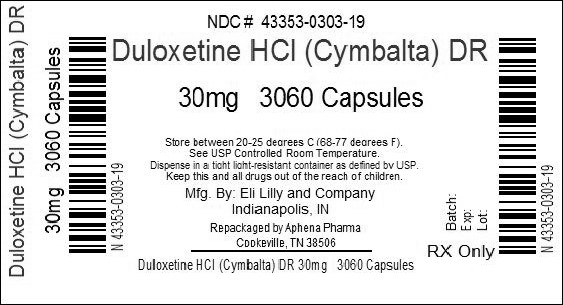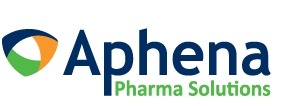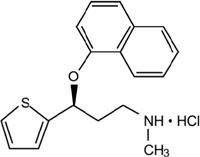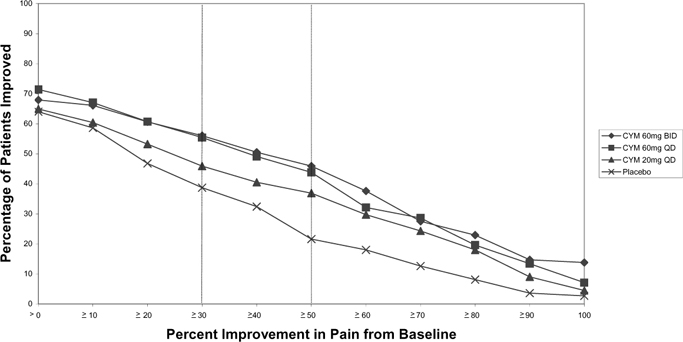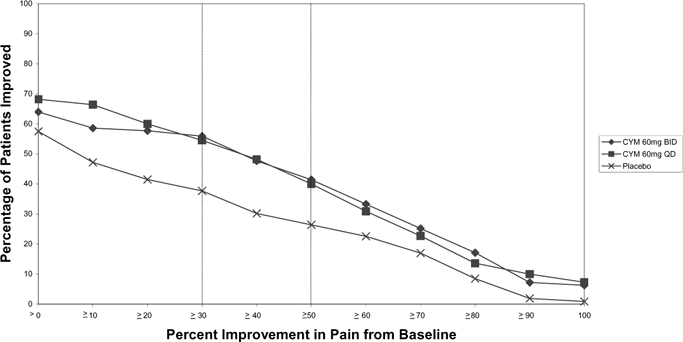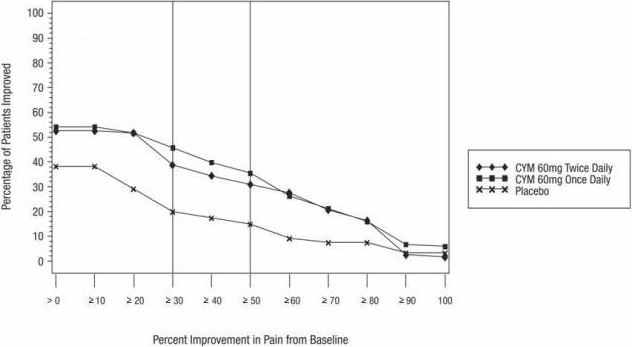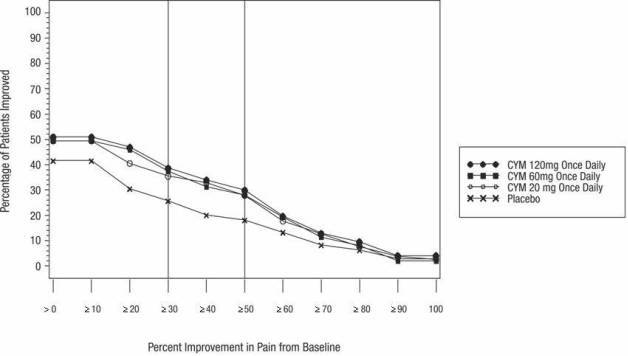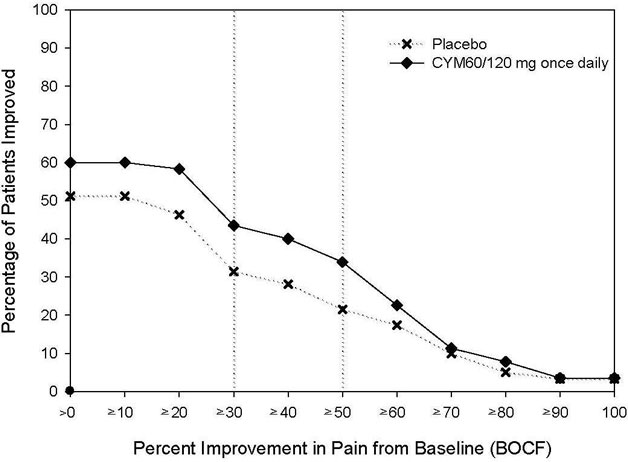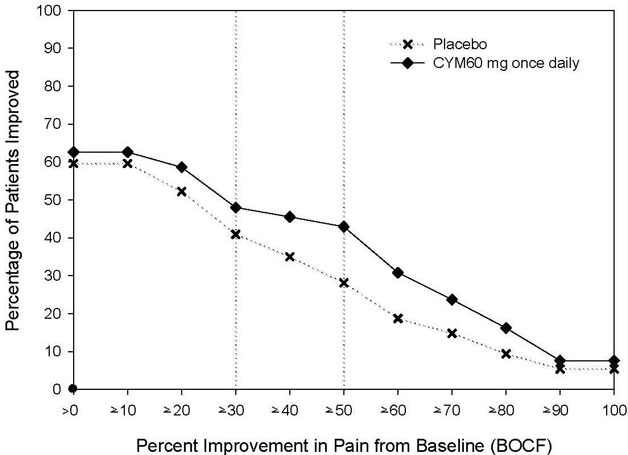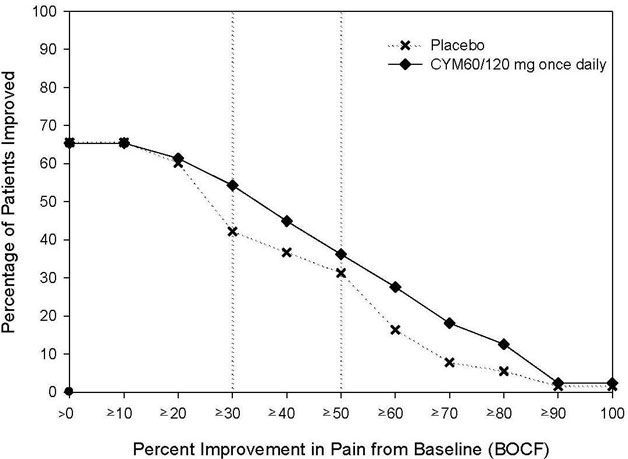 DRUG LABEL: Cymbalta
NDC: 43353-303 | Form: CAPSULE, DELAYED RELEASE
Manufacturer: Aphena Pharma Solutions - Tennessee, LLC
Category: prescription | Type: HUMAN PRESCRIPTION DRUG LABEL
Date: 20140414

ACTIVE INGREDIENTS: Duloxetine hydrochloride 30 mg/1 1
INACTIVE INGREDIENTS: Gelatin; Hypromelloses; HYPROMELLOSE ACETATE SUCCINATE 16070722 (3 MM2/S); Sodium lauryl sulfate; Sucrose; Talc; Titanium dioxide; Triethyl citrate; FD&C BLUE NO. 2

HIGHLIGHTS OF PRESCRIBING INFORMATION

These highlights do not include all the information needed to use CYMBALTA safely and effectively. See full prescribing information for CYMBALTA.
CYMBALTA (Duloxetine Delayed-Release Capsules) for Oral Use.
Initial U.S. Approval: 2004

RECENT MAJOR CHANGES

Dosage and Administration:

Switching a Patient To or From a Monoamine Oxidase Inhibitor (MAOI) Intended
to Treat Psychiatric Disorders (2.5) 10/2012

Use of Cymbalta with Other MAOIs such as Linezolid or
Methylene Blue (2.6) 10/2012

Contraindications:

Monoamine Oxidase Inhibitors (4.1) 10/2012

Warnings and Precautions:

Hepatotoxicity (5.2) 09/2012

Serotonin Syndrome (5.4) 10/2012

Discontinuation of Treatment with Cymbalta (5.7) 08/2012

Activation of Mania/Hypomania (5.8) 09/2012

Seizures (5.9) 09/2012

WARNING: SUICIDAL THOUGHTS AND BEHAVIORS

WARNING: SUICIDALTHOUGHTS AND BEHAVIORS

See full prescribing information for complete boxed warning.

- Increased risk of suicidal thinking and behavior in children, adolescents, and young adults taking antidepressants (5.1)
- Monitor for worsening and emergence of suicidal thoughts and behaviors (5.1)
- Cymbalta is not approved for use in pediatric patients (8.4)

1 INDICATIONS AND USAGE

Cymbalta® is a serotonin and norepinephrine reuptake inhibitor (SNRI) indicated for:

- Major Depressive Disorder (MDD) (1.1)
- Generalized Anxiety Disorder (GAD) (1.2)
- Diabetic Peripheral Neuropathic Pain (DPNP) (1.3)
- Fibromyalgia (FM) (1.4)
- Chronic Musculoskeletal Pain (1.5)

2 DOSAGE AND ADMINISTRATION

- Cymbalta should generally be administered once daily without regard to meals. Cymbalta should be swallowed whole and should not be chewed or crushed, nor should the capsule be opened and its contents be sprinkled on food or mixed with liquids (2)

Indication | Starting Dose | Target Dose | Maximum Dose
MDD (2.1, 2.2) | 40 mg/day to 60 mg/day | Acute Treatment: 40 mg/day (20 mg twice daily) to 60 mg/day (once daily or as 30 mg twice daily); Maintenance Treatment: 60 mg/day | 120 mg/day
GAD (2.1) | 60 mg/day | 60 mg/day (once daily) | 120 mg/day
DPNP (2.1) | 60 mg/day | 60 mg/day (once daily) | 60 mg/day
FM (2.1) | 30 mg/day | 60 mg/day (once daily) | 60 mg/day
Chronic Musculoskeletal Pain (2.1) | 30 mg/day | 60 mg/day (once daily) | 60 mg/day

- Some patients may benefit from starting at 30 mg once daily (2.1)
- There is no evidence that doses greater than 60 mg/day confers additional benefit, while some adverse reactions were observed to be dose-dependent (2.1)
- Discontinuing Cymbalta: A gradual dose reduction is recommended to avoid discontinuation symptoms (2.4, 5.7)

3 DOSAGE FORMS AND STRENGTHS

20 mg, 30 mg, and 60 mg capsules (3)

4 CONTRAINDICATIONS

- Serotonin Syndrome and MAOIs: Do not use MAOIs intended to treat psychiatric disorders with Cymbalta or within 5 days of stopping treatment with Cymbalta. Do not use Cymbalta within 14 days of stopping an MAOI intended to treat psychiatric disorders. In addition, do not start Cymbalta in a patient who is being treated with linezolid or intravenous methylene blue (4.1)
- Use in patients with uncontrolled narrow-angle glaucoma (4.2)

5 WARNINGS AND PRECAUTIONS

- Suicidality: Monitor for clinical worsening and suicide risk (5.1)
- Hepatotoxicity: Hepatic failure, sometimes fatal, has been reported in patients treated with Cymbalta. Cymbalta should be discontinued in patients who develop jaundice or other evidence of clinically significant liver dysfunction and should not be resumed unless another cause can be established. Cymbalta should not be prescribed to patients with substantial alcohol use or evidence of chronic liver disease (5.2)
- Orthostatic Hypotension and Syncope: Cases have been reported with duloxetine therapy (5.3)
- Serotonin Syndrome: Serotonin syndrome has been reported with SSRIs and SNRIs, including with Cymbalta, both when taken alone, but especially when co-administered with other serotonergic agents (including triptans, tricyclic antidepressants, fentanyl, lithium, tramadol, tryptophan, buspirone and St. John's Wort). If such symptoms occur, discontinue Cymbalta and initiate supportive treatment. If concomitant use of Cymbalta with other serotonergic drugs is clinically warranted, patients should be made aware of a potential increased risk for serotonin syndrome, particularly during treatment initiation and dose increases (5.4)
- Abnormal Bleeding: Cymbalta may increase the risk of bleeding events. Patients should be cautioned about the risk of bleeding associated with the concomitant use of duloxetine and NSAIDs, aspirin, or other drugs that affect coagulation (5.5, 7.4)
- Severe Skin Reactions: Severe skin reactions, including erythema multiforme and Stevens-Johnson Syndrome (SJS), can occur with Cymbalta. Cymbalta should be discontinued at the first appearance of blisters, peeling rash, mucosal erosions, or any other sign of hypersensitivity if no other etiology can be identified. (5.6)
- Discontinuation: May result in symptoms, including dizziness, headache, nausea, diarrhea, paresthesia, irritability, vomiting, insomnia, anxiety, hyperhidrosis, and fatigue (5.7)
- Activation of mania or hypomania has occurred (5.8)
- Seizures: Prescribe with care in patients with a history of seizure disorder (5.9)
- Blood Pressure: Monitor blood pressure prior to initiating treatment and periodically throughout treatment (5.10)
- Inhibitors of CYP1A2 or Thioridazine: Should not administer with Cymbalta (5.11)
- Hyponatremia: Cases of hyponatremia have been reported (5.12)
- Hepatic Insufficiency and Severe Renal Impairment: Should ordinarily not be administered to these patients (5.13)
- Controlled Narrow-Angle Glaucoma: Use cautiously in these patients (5.13)
- Glucose Control in Diabetes: In diabetic peripheral neuropathic pain patients, small increases in fasting blood glucose, and HbA1c have been observed (5.13)
- Conditions that Slow Gastric Emptying: Use cautiously in these patients (5.13)
- Urinary Hesitation and Retention (5.14)

6 ADVERSE REACTIONS

- Most common adverse reactions (≥5% and at least twice the incidence of placebo patients): nausea, dry mouth, somnolence, constipation, decreased appetite, and hyperhidrosis (6.3).

To report SUSPECTED ADVERSE REACTIONS, contact Eli Lilly and Company at 1-800-LillyRx (1-800-545-5979) or FDA at 1-800-FDA-1088 or www.fda.gov/medwatch.

7 DRUG INTERACTIONS

- Potent inhibitors of CYP1A2 should be avoided (7.1).
- Potent inhibitors of CYP2D6 may increase duloxetine concentrations (7.2).
- Duloxetine is a moderate inhibitor of CYP2D6 (7.9).

8 USE IN SPECIFIC POPULATIONS

- Pregnancy and Nursing Mothers: Use only if the potential benefit justifies the potential risk to the fetus or child (2.3, 8.1, 8.3).

FULL PRESCRIBING INFORMATION

WARNING: SUICIDAL THOUGHTS AND BEHAVIORS

Antidepressants increased the risk of suicidal thoughts and behavior in children, adolescents, and young adults in short-term studies. These studies did not show an increase in the risk of suicidal thoughts and behavior with antidepressant use in patients over age 24; there was a reduction in risk with antidepressant use in patients aged 65 and older [see Warnings and Precautions (5.1)].

In patients of all ages who are started on antidepressant therapy, monitor closely for worsening, and for emergence of suicidal thoughts and behaviors. Advise families and caregivers of the need for close observation and communication with the prescriber [see Warnings and Precautions (5.1)].

Cymbalta is not approved for use in pediatric patients [see Use in Specific Populations (8.4)].

1 INDICATIONS AND USAGE

1.1 Major Depressive Disorder

Cymbalta is indicated for the treatment of major depressive disorder (MDD). The efficacy of Cymbalta was established in four short-term and one maintenance trial in adults [see Clinical Studies (14.1)].

A major depressive episode (DSM-IV) implies a prominent and relatively persistent (nearly every day for at least 2 weeks) depressed or dysphoric mood that usually interferes with daily functioning, and includes at least 5 of the following 9 symptoms: depressed mood, loss of interest in usual activities, significant change in weight and/or appetite, insomnia or hypersomnia, psychomotor agitation or retardation, increased fatigue, feelings of guilt or worthlessness, slowed thinking or impaired concentration, or a suicide attempt or suicidal ideation.

1.2 Generalized Anxiety Disorder

Cymbalta is indicated for the treatment of generalized anxiety disorder (GAD). The efficacy of Cymbalta was established in three short-term trials and one maintenance trial in adults [see Clinical Studies (14.2)].

Generalized anxiety disorder is defined by the DSM-IV as excessive anxiety and worry, present more days than not, for at least 6 months. The excessive anxiety and worry must be difficult to control and must cause significant distress or impairment in normal functioning. It must be associated with at least 3 of the following 6 symptoms: restlessness or feeling keyed up or on edge, being easily fatigued, difficulty concentrating or mind going blank, irritability, muscle tension, and/or sleep disturbance.

1.3 Diabetic Peripheral Neuropathic Pain

Cymbalta is indicated for the management of neuropathic pain (DPNP) associated with diabetic peripheral neuropathy [see Clinical Studies (14.3)].

1.4 Fibromyalgia

Cymbalta is indicated for the management of fibromyalgia (FM) [see Clinical Studies (14.4)].

1.5 Chronic Musculoskeletal Pain

Cymbalta is indicated for the management of chronic musculoskeletal pain. This has been established in studies in patients with chronic low back pain (CLBP) and chronic pain due to osteoarthritis [see Clinical Studies (14.5)].

2 DOSAGE AND ADMINISTRATION

Cymbalta should be swallowed whole and should not be chewed or crushed, nor should the capsule be opened and its contents sprinkled on food or mixed with liquids. All of these might affect the enteric coating. Cymbalta can be given without regard to meals.

2.1 Initial Treatment

Major Depressive Disorder — Cymbalta should be administered at a total dose of 40 mg/day (given as 20 mg twice daily) to 60 mg/day (given either once daily or as 30 mg twice daily). For some patients, it may be desirable to start at 30 mg once daily for 1 week, to allow patients to adjust to the medication before increasing to 60 mg once daily. While a 120 mg/day dose was shown to be effective, there is no evidence that doses greater than 60 mg/day confer any additional benefits. The safety of doses above 120 mg/day has not been adequately evaluated [see Clinical Studies (14.1)].

Generalized Anxiety Disorder — For most patients, the recommended starting dose for Cymbalta is 60 mg administered once daily. For some patients, it may be desirable to start at 30 mg once daily for 1 week, to allow patients to adjust to the medication before increasing to 60 mg once daily. While a 120 mg once daily dose was shown to be effective, there is no evidence that doses greater than 60 mg/day confer additional benefit. Nevertheless, if a decision is made to increase the dose beyond 60 mg once daily, dose increases should be in increments of 30 mg once daily. The safety of doses above 120 mg once daily has not been adequately evaluated [see Clinical Studies (14.2)].

Diabetic Peripheral Neuropathic Pain — The recommended dose for Cymbalta is 60 mg administered once daily. There is no evidence that doses higher than 60 mg confer additional significant benefit and the higher dose is clearly less well tolerated [see Clinical Studies (14.3)]. For patients for whom tolerability is a concern, a lower starting dose may be considered.

Since diabetes is frequently complicated by renal disease, a lower starting dose and gradual increase in dose should be considered for patients with renal impairment [see Dosage and Administration (2.3), Use in Specific Populations (8.10), and Clinical Pharmacology (12.3)].

Fibromyalgia — The recommended dose for Cymbalta is 60 mg administered once daily. Treatment should begin at 30 mg once daily for 1 week, to allow patients to adjust to the medication before increasing to 60 mg once daily. Some patients may respond to the starting dose. There is no evidence that doses greater than 60 mg/day confer additional benefit, even in patients who do not respond to a 60 mg dose, and higher doses are associated with a higher rate of adverse reactions [see Clinical Studies (14.4)].

Chronic Musculoskeletal Pain — The recommended dose for Cymbalta is 60 mg once daily. Dosing may be started at 30 mg for one week, to allow patients to adjust to the medication before increasing to 60 mg once daily. There is no evidence that higher doses confer additional benefit, even in patients who do not respond to a 60 mg dose, and higher doses are associated with a higher rate of adverse reactions [see Clinical Studies (14.5)].

2.2 Maintenance/Continuation/Extended Treatment

Major Depressive Disorder — It is generally agreed that acute episodes of major depression require several months or longer of sustained pharmacologic therapy. Maintenance of efficacy in MDD was demonstrated with Cymbalta as monotherapy. Cymbalta should be administered at a total dose of 60 mg once daily. Patients should be periodically reassessed to determine the need for maintenance treatment and the appropriate dose for such treatment [see Clinical Studies (14.1)].

Generalized Anxiety Disorder — It is generally agreed that episodes of generalized anxiety disorder require several months or longer of sustained pharmacological therapy. Maintenance of efficacy in GAD was demonstrated with Cymbalta as monotherapy. Cymbalta should be administered in a dose range of 60-120 mg once daily. Patients should be periodically reassessed to determine the continued need for maintenance treatment and the appropriate dose for such treatment [see Clinical Studies (14.2)].

Diabetic Peripheral Neuropathic Pain — As the progression of diabetic peripheral neuropathy is highly variable and management of pain is empirical, the effectiveness of Cymbalta must be assessed individually. Efficacy beyond 12 weeks has not been systematically studied in placebo-controlled trials.

Fibromyalgia — Fibromyalgia is recognized as a chronic condition. The efficacy of Cymbalta in the management of fibromyalgia has been demonstrated in placebo-controlled studies up to 3 months. The efficacy of Cymbalta was not demonstrated in longer studies; however, continued treatment should be based on individual patient response.

Chronic Musculoskeletal Pain — The efficacy of Cymbalta has not been established in placebo-controlled studies beyond 13 weeks.

2.3 Dosing in Special Populations

Hepatic Insufficiency — It is recommended that Cymbalta should ordinarily not be administered to patients with any hepatic insufficiency [see Warnings and Precautions (5.13) and Use in Specific Populations (8.9)].

Severe Renal Impairment — Cymbalta is not recommended for patients with end-stage renal disease or severe renal impairment (estimated creatinine clearance <30 mL/min) [see Warnings and Precautions (5.13) and Use in Specific Populations (8.10)].

Elderly Patients — No dose adjustment is recommended for elderly patients on the basis of age. As with any drug, caution should be exercised in treating the elderly. When individualizing the dosage in elderly patients, extra care should be taken when increasing the dose [see Use in Specific Populations (8.5)].

Pregnant Women — There are no adequate and well-controlled studies in pregnant women; therefore, Cymbalta should be used during pregnancy only if the potential benefit justifies the potential risk to the fetus [see Use in Specific Populations (8.1)].

Lilly maintains a pregnancy registry to monitor the pregnancy outcomes of women exposed to Cymbalta while pregnant. Healthcare providers are encouraged to register any patient who is exposed to Cymbalta during pregnancy by calling the Cymbalta Pregnancy Registry at 1-866-814-6975 or by visiting www.cymbaltapregnancyregistry.com

Nursing Mothers — Because the safety of duloxetine in infants is not known, nursing while on Cymbalta is not recommended [see Use in Specific Populations (8.3)].

2.4 Discontinuing Cymbalta

Symptoms associated with discontinuation of Cymbalta and other SSRIs and SNRIs have been reported. A gradual reduction in the dose rather than abrupt cessation is recommended whenever possible [see Warnings and Precautions (5.7)].

2.5 Switching a Patient To or From a Monoamine Oxidase Inhibitor (MAOI) Intended to Treat Psychiatric Disorders

At least 14 days should elapse between discontinuation of an MAOI intended to treat psychiatric disorders and initiation of therapy with Cymbalta. Conversely, at least 5 days should be allowed after stopping Cymbalta before starting an MAOI intended to treat psychiatric disorders [see Contraindications (4.1)].

2.6 Use of Cymbalta with Other MAOIs such as Linezolid or Methylene Blue

Do not start Cymbalta in a patient who is being treated with linezolid or intravenous methylene blue because there is an increased risk of serotonin syndrome. In a patient who requires more urgent treatment of a psychiatric condition, other interventions, including hospitalization, should be considered [see Contraindications (4.1)].

In some cases, a patient already receiving Cymbalta therapy may require urgent treatment with linezolid or intravenous methylene blue. If acceptable alternatives to linezolid or intravenous methylene blue treatment are not available and the potential benefits of linezolid or intravenous methylene blue treatment are judged to outweigh the risks of serotonin syndrome in a particular patient, Cymbalta should be stopped promptly, and linezolid or intravenous methylene blue can be administered. The patient should be monitored for symptoms of serotonin syndrome for 5 days or until 24 hours after the last dose of linezolid or intravenous methylene blue, whichever comes first. Therapy with Cymbalta may be resumed 24 hours after the last dose of linezolid or intravenous methylene blue [see Warnings and Precautions (5.4)].

The risk of administering methylene blue by non-intravenous routes (such as oral tablets or by local injection) or in intravenous doses much lower than 1 mg/kg with Cymbalta is unclear. The clinician should, nevertheless, be aware of the possibility of emergent symptoms of serotonin syndrome with such use [see Warnings and Precautions (5.4)].

3 DOSAGE FORMS AND STRENGTHS

Cymbalta is available as delayed release capsules:

20 mg opaque green capsules imprinted with “Lilly 3235 20mg”

30 mg opaque white and blue capsules imprinted with “Lilly 3240 30mg”

60 mg opaque green and blue capsules imprinted with “Lilly 3270 60mg”

4 CONTRAINDICATIONS

4.1 Monoamine Oxidase Inhibitors (MAOIs)

The use of MAOIs intended to treat psychiatric disorders with Cymbalta or within 5 days of stopping treatment with Cymbalta is contraindicated because of an increased risk of serotonin syndrome. The use of Cymbalta within 14 days of stopping an MAOI intended to treat psychiatric disorders is also contraindicated [see Dosage and Administration (2.5) and Warnings and Precautions (5.4)].

Starting Cymbalta in a patient who is being treated with MAOIs such as linezolid or intravenous methylene blue is also contraindicated because of an increased risk of serotonin syndrome [see Dosage and Administration (2.6) and Warnings and Precautions (5.4)].

4.2 Uncontrolled Narrow-Angle Glaucoma

In clinical trials, Cymbalta use was associated with an increased risk of mydriasis; therefore, its use should be avoided in patients with uncontrolled narrow-angle glaucoma [see Warnings and Precautions (5.13)].

5 WARNINGS AND PRECAUTIONS

5.1 Suicidal Thoughts and Behaviors in Adolescents and Young Adults

Patients with major depressive disorder (MDD), both adult and pediatric, may experience worsening of their depression and/or the emergence of suicidal ideation and behavior (suicidality) or unusual changes in behavior, whether or not they are taking antidepressant medications, and this risk may persist until significant remission occurs. Suicide is a known risk of depression and certain other psychiatric disorders, and these disorders themselves are the strongest predictors of suicide. There has been a long-standing concern, however, that antidepressants may have a role in inducing worsening of depression and the emergence of suicidality in certain patients during the early phases of treatment.

Pooled analyses of short-term placebo-controlled trials of antidepressant drugs (SSRIs and others) showed that these drugs increase the risk of suicidal thinking and behavior (suicidality) in children, adolescents, and young adults (ages 18-24) with major depressive disorder (MDD) and other psychiatric disorders. Short-term studies did not show an increase in the risk of suicidality with antidepressants compared to placebo in adults beyond age 24; there was a reduction with antidepressants compared to placebo in adults aged 65 and older.

The pooled analyses of placebo-controlled trials in children and adolescents with MDD, obsessive compulsive disorder (OCD), or other psychiatric disorders included a total of 24 short-term trials of 9 antidepressant drugs in over 4400 patients. The pooled analyses of placebo-controlled trials in adults with MDD or other psychiatric disorders included a total of 295 short-term trials (median duration of 2 months) of 11 antidepressant drugs in over 77,000 patients. There was considerable variation in risk of suicidality among drugs, but a tendency toward an increase in the younger patients for almost all drugs studied. There were differences in absolute risk of suicidality across the different indications, with the highest incidence in MDD. The risk of differences (drug vs placebo), however, were relatively stable within age strata and across indications. These risk differences (drug-placebo difference in the number of cases of suicidality per 1000 patients treated) are provided in Table 1.

Table 1
Age Range | Drug-Placebo Difference in Number of Cases of Suicidality per 1000 Patients Treated
 | Increases Compared to Placebo
<18 | 14 additional cases
18-24 | 5 additional cases
 | Decreases Compared to Placebo
25-64 | 1 fewer case
≥65 | 6 fewer cases

No suicides occurred in any of the pediatric trials. There were suicides in the adult trials, but the number was not sufficient to reach any conclusion about drug effect on suicide.

It is unknown whether the suicidality risk extends to longer-term use, i.e., beyond several months. However, there is substantial evidence from placebo-controlled maintenance trials in adults with depression that the use of antidepressants can delay the recurrence of depression.

All patients being treated with antidepressants for any indication should be monitored appropriately and observed closely for clinical worsening, suicidality, and unusual changes in behavior, especially during the initial few months of a course of drug therapy, or at times of dose changes, either increases or decreases.

The following symptoms, anxiety, agitation, panic attacks, insomnia, irritability, hostility, aggressiveness, impulsivity, akathisia (psychomotor restlessness), hypomania, and mania, have been reported in adult and pediatric patients being treated with antidepressants for major depressive disorder as well as for other indications, both psychiatric and nonpsychiatric. Although a causal link between the emergence of such symptoms and either the worsening of depression and/or the emergence of suicidal impulses has not been established, there is concern that such symptoms may represent precursors to emerging suicidality.

Consideration should be given to changing the therapeutic regimen, including possibly discontinuing the medication, in patients whose depression is persistently worse, or who are experiencing emergent suicidality or symptoms that might be precursors to worsening depression or suicidality, especially if these symptoms are severe, abrupt in onset, or were not part of the patient's presenting symptoms.

If the decision has been made to discontinue treatment, medication should be tapered, as rapidly as is feasible, but with recognition that discontinuation can be associated with certain symptoms [see Dosage and Administration (2.4) and Warnings and Precautions (5.7) for descriptions of the risks of discontinuation of Cymbalta].

Families and caregivers of patients being treated with antidepressants for major depressive disorder or other indications, both psychiatric and nonpsychiatric, should be alerted about the need to monitor patients for the emergence of agitation, irritability, unusual changes in behavior, and the other symptoms described above, as well as the emergence of suicidality, and to report such symptoms immediately to health care providers. Such monitoring should include daily observation by families and caregivers. Prescriptions for Cymbalta should be written for the smallest quantity of capsules consistent with good patient management, in order to reduce the risk of overdose.

Screening Patients for Bipolar Disorder — A major depressive episode may be the initial presentation of bipolar disorder. It is generally believed (though not established in controlled trials) that treating such an episode with an antidepressant alone may increase the likelihood of precipitation of a mixed/manic episode in patients at risk for bipolar disorder. Whether any of the symptoms described above represent such a conversion is unknown. However, prior to initiating treatment with an antidepressant, patients with depressive symptoms should be adequately screened to determine if they are at risk for bipolar disorder; such screening should include a detailed psychiatric history, including a family history of suicide, bipolar disorder, and depression. It should be noted that Cymbalta (duloxetine) is not approved for use in treating bipolar depression.

5.2 Hepatotoxicity

There have been reports of hepatic failure, sometimes fatal, in patients treated with Cymbalta. These cases have presented as hepatitis with abdominal pain, hepatomegaly, and elevation of transaminase levels to more than twenty times the upper limit of normal with or without jaundice, reflecting a mixed or hepatocellular pattern of liver injury. Cymbalta should be discontinued in patients who develop jaundice or other evidence of clinically significant liver dysfunction and should not be resumed unless another cause can be established.

Cases of cholestatic jaundice with minimal elevation of transaminase levels have also been reported. Other postmarketing reports indicate that elevated transaminases, bilirubin, and alkaline phosphatase have occurred in patients with chronic liver disease or cirrhosis.

Cymbalta increased the risk of elevation of serum transaminase levels in development program clinical trials. Liver transaminase elevations resulted in the discontinuation of 0.3% (92/34,756) of Cymbalta-treated patients. In most patients, the median time to detection of the transaminase elevation was about two months. In placebo-controlled trials in any indication, for patients with normal and abnormal baseline ALT values, elevation of ALT >3 times the upper limit of normal occurred in 1.25% (144/11,496) of Cymbalta-treated patients compared to 0.45% (39/8716) of placebo-treated patients. In placebo-controlled studies using a fixed dose design, there was evidence of a dose response relationship for ALT and AST elevation of >3 times the upper limit of normal and >5 times the upper limit of normal, respectively.

Because it is possible that duloxetine and alcohol may interact to cause liver injury or that duloxetine may aggravate pre-existing liver disease, Cymbalta should not be prescribed to patients with substantial alcohol use or evidence of chronic liver disease.

5.3 Orthostatic Hypotension and Syncope

Orthostatic hypotension and syncope have been reported with therapeutic doses of duloxetine. Syncope and orthostatic hypotension tend to occur within the first week of therapy but can occur at any time during duloxetine treatment, particularly after dose increases. The risk of blood pressure decreases may be greater in patients taking concomitant medications that induce orthostatic hypotension (such as antihypertensives) or are potent CYP1A2 inhibitors [see Warnings and Precautions (5.11) and Drug Interactions (7.1)] and in patients taking duloxetine at doses above 60 mg daily. Consideration should be given to discontinuing duloxetine in patients who experience symptomatic orthostatic hypotension and/or syncope during duloxetine therapy.

5.4 Serotonin Syndrome

The development of a potentially life-threatening serotonin syndrome has been reported with SNRIs and SSRIs, including Cymbalta, alone but particularly with concomitant use of other serotonergic drugs (including triptans, tricyclic antidepressants, fentanyl, lithium, tramadol, tryptophan, buspirone, and St. John's Wort) and with drugs that impair metabolism of serotonin (in particular, MAOIs, both those intended to treat psychiatric disorders and also others, such as linezolid and intravenous methylene blue).

Serotonin syndrome symptoms may include mental status changes (e.g., agitation, hallucinations, delirium, and coma), autonomic instability (e.g., tachycardia, labile blood pressure, dizziness, diaphoresis, flushing, hyperthermia), neuromuscular symptoms (e.g., tremor, rigidity, myoclonus, hyperreflexia, incoordination), seizures, and/or gastrointestinal symptoms (e.g., nausea, vomiting, diarrhea). Patients should be monitored for the emergence of serotonin syndrome.

The concomitant use of Cymbalta with MAOIs intended to treat psychiatric disorders is contraindicated. Cymbalta should also not be started in a patient who is being treated with MAOIs such as linezolid or intravenous methylene blue. All reports with methylene blue that provided information on the route of administration involved intravenous administration in the dose range of 1 mg/kg to 8 mg/kg. No reports involved the administration of methylene blue by other routes (such as oral tablets or local tissue injection) or at lower doses. There may be circumstances when it is necessary to initiate treatment with an MAOI such as linezolid or intravenous methylene blue in a patient taking Cymbalta. Cymbalta should be discontinued before initiating treatment with the MAOI [see Dosage and Administration (2.5, 2.6), and Contraindications (4.1)].

If concomitant use of Cymbalta with other serotonergic drugs including triptans, tricyclic antidepressants, fentanyl, lithium, tramadol, buspirone, tryptophan and St. John's Wort is clinically warranted, patients should be made aware of a potential increased risk for serotonin syndrome, particularly during treatment initiation and dose increases. Treatment with Cymbalta and any concomitant serotonergic agents, should be discontinued immediately if the above events occur and supportive symptomatic treatment should be initiated.

5.5 Abnormal Bleeding

SSRIs and SNRIs, including duloxetine, may increase the risk of bleeding events. Concomitant use of aspirin, nonsteroidal anti-inflammatory drugs, warfarin, and other anti-coagulants may add to this risk. Case reports and epidemiological studies (case-control and cohort design) have demonstrated an association between use of drugs that interfere with serotonin reuptake and the occurrence of gastrointestinal bleeding. Bleeding events related to SSRIs and SNRIs use have ranged from ecchymoses, hematomas, epistaxis, and petechiae to life-threatening hemorrhages.

Patients should be cautioned about the risk of bleeding associated with the concomitant use of duloxetine and NSAIDs, aspirin, or other drugs that affect coagulation.

5.6 Severe Skin Reactions

Severe skin reactions, including erythema multiforme and Stevens-Johnson Syndrome (SJS), can occur with Cymbalta. The reporting rate of SJS associated with Cymbalta use exceeds the general population background incidence rate for this serious skin reaction (1 to 2 cases per million person years). The reporting rate is generally accepted to be an underestimate due to underreporting.

Cymbalta should be discontinued at the first appearance of blisters, peeling rash, mucosal erosions, or any other sign of hypersensitivity if no other etiology can be identified.

5.7 Discontinuation of Treatment with Cymbalta

Discontinuation symptoms have been systematically evaluated in patients taking duloxetine. Following abrupt or tapered discontinuation in placebo-controlled clinical trials, the following symptoms occurred at 1% or greater and at a significantly higher rate in duloxetine-treated patients compared to those discontinuing from placebo: dizziness, headache, nausea, diarrhea, paresthesia, irritability, vomiting, insomnia, anxiety, hyperhidrosis, and fatigue.

During marketing of other SSRIs and SNRIs (serotonin and norepinephrine reuptake inhibitors), there have been spontaneous reports of adverse events occurring upon discontinuation of these drugs, particularly when abrupt, including the following: dysphoric mood, irritability, agitation, dizziness, sensory disturbances (e.g., paresthesias such as electric shock sensations), anxiety, confusion, headache, lethargy, emotional lability, insomnia, hypomania, tinnitus, and seizures. Although these events are generally self-limiting, some have been reported to be severe.

Patients should be monitored for these symptoms when discontinuing treatment with Cymbalta. A gradual reduction in the dose rather than abrupt cessation is recommended whenever possible. If intolerable symptoms occur following a decrease in the dose or upon discontinuation of treatment, then resuming the previously prescribed dose may be considered. Subsequently, the physician may continue decreasing the dose but at a more gradual rate [see Dosage and Administration (2.4)].

5.8 Activation of Mania/Hypomania

In placebo-controlled trials in patients with major depressive disorder, activation of mania or hypomania was reported in 0.1% (4/3779) of duloxetine-treated patients and 0.04% (1/2536) of placebo-treated patients. No activation of mania or hypomania was reported in GAD, fibromyalgia, or chronic musculoskeletal pain placebo-controlled trials. Activation of mania or hypomania has been reported in a small proportion of patients with mood disorders who were treated with other marketed drugs effective in the treatment of major depressive disorder. As with these other agents, Cymbalta should be used cautiously in patients with a history of mania.

5.9 Seizures

Duloxetine has not been systematically evaluated in patients with a seizure disorder, and such patients were excluded from clinical studies. In placebo-controlled clinical trials, seizures/convulsions occurred in 0.02% (3/12,722) of patients treated with duloxetine and 0.01% (1/9513) of patients treated with placebo. Cymbalta should be prescribed with care in patients with a history of a seizure disorder.

5.10 Effect on Blood Pressure

In placebo-controlled clinical trials across indications from baseline to endpoint, duloxetine treatment was associated with mean increases of 0.5 mm Hg in systolic blood pressure and 0.8 mm Hg in diastolic blood pressure compared to mean decreases of 0.6 mm Hg systolic and 0.3 mm Hg diastolic in placebo-treated patients. There was no significant difference in the frequency of sustained (3 consecutive visits) elevated blood pressure. In a clinical pharmacology study designed to evaluate the effects of duloxetine on various parameters, including blood pressure at supratherapeutic doses with an accelerated dose titration, there was evidence of increases in supine blood pressure at doses up to 200 mg twice daily. At the highest 200 mg twice daily dose, the increase in mean pulse rate was 5.0 to 6.8 beats and increases in mean blood pressure were 4.7 to 6.8 mm Hg (systolic) and 4.5 to 7 mm Hg (diastolic) up to 12 hours after dosing.

Blood pressure should be measured prior to initiating treatment and periodically measured throughout treatment [see Adverse Reactions (6.7)].

5.11 Clinically Important Drug Interactions

Both CYP1A2 and CYP2D6 are responsible for duloxetine metabolism.

Potential for Other Drugs to Affect Cymbalta

CYP1A2 Inhibitors — Co-administration of Cymbalta with potent CYP1A2 inhibitors should be avoided [see Drug Interactions (7.1)].

CYP2D6 Inhibitors — Because CYP2D6 is involved in duloxetine metabolism, concomitant use of duloxetine with potent inhibitors of CYP2D6 would be expected to, and does, result in higher concentrations (on average of 60%) of duloxetine [see Drug Interactions (7.2)].

Potential for Cymbalta to Affect Other Drugs

Drugs Metabolized by CYP2D6 — Co-administration of Cymbalta with drugs that are extensively metabolized by CYP2D6 and that have a narrow therapeutic index, including certain antidepressants (tricyclic antidepressants [TCAs], such as nortriptyline, amitriptyline, and imipramine), phenothiazines and Type 1C antiarrhythmics (e.g., propafenone, flecainide), should be approached with caution. Plasma TCA concentrations may need to be monitored and the dose of the TCA may need to be reduced if a TCA is co-administered with Cymbalta. Because of the risk of serious ventricular arrhythmias and sudden death potentially associated with elevated plasma levels of thioridazine, Cymbalta and thioridazine should not be co-administered [see Drug Interactions (7.9)].

Other Clinically Important Drug Interactions

Alcohol — Use of Cymbalta concomitantly with heavy alcohol intake may be associated with severe liver injury. For this reason, Cymbalta should not be prescribed for patients with substantial alcohol use [see Warnings and Precautions (5.2) and Drug Interactions (7.15)].

CNS Acting Drugs — Given the primary CNS effects of Cymbalta, it should be used with caution when it is taken in combination with or substituted for other centrally acting drugs, including those with a similar mechanism of action [see Warnings and Precautions (5.11) and Drug Interactions (7.16)].

5.12 Hyponatremia

Hyponatremia may occur as a result of treatment with SSRIs and SNRIs, including Cymbalta. In many cases, this hyponatremia appears to be the result of the syndrome of inappropriate antidiuretic hormone secretion (SIADH). Cases with serum sodium lower than 110 mmol/L have been reported and appeared to be reversible when Cymbalta was discontinued. Elderly patients may be at greater risk of developing hyponatremia with SSRIs and SNRIs. Also, patients taking diuretics or who are otherwise volume depleted may be at greater risk [see Use in Specific Populations (8.5)]. Discontinuation of Cymbalta should be considered in patients with symptomatic hyponatremia and appropriate medical intervention should be instituted.

Signs and symptoms of hyponatremia include headache, difficulty concentrating, memory impairment, confusion, weakness, and unsteadiness, which may lead to falls. More severe and/or acute cases have been associated with hallucination, syncope, seizure, coma, respiratory arrest, and death.

5.13 Use in Patients with Concomitant Illness

Clinical experience with Cymbalta in patients with concomitant systemic illnesses is limited. There is no information on the effect that alterations in gastric motility may have on the stability of Cymbalta's enteric coating. In extremely acidic conditions, Cymbalta, unprotected by the enteric coating, may undergo hydrolysis to form naphthol. Caution is advised in using Cymbalta in patients with conditions that may slow gastric emptying (e.g., some diabetics).

Cymbalta has not been systematically evaluated in patients with a recent history of myocardial infarction or unstable coronary artery disease. Patients with these diagnoses were generally excluded from clinical studies during the product's premarketing testing.

Hepatic Insufficiency — Cymbalta should ordinarily not be used in patients with hepatic insufficiency [see Dosage and Administration (2.3), Warnings and Precautions (5.2), and Use in Specific Populations (8.9)].

Severe Renal Impairment — Cymbalta should ordinarily not be used in patients with end-stage renal disease or severe renal impairment (creatinine clearance <30 mL/min). Increased plasma concentration of duloxetine, and especially of its metabolites, occur in patients with end-stage renal disease (requiring dialysis) [see Dosage and Administration (2.3) and Use in Specific Populations (8.10)].

Controlled Narrow-Angle Glaucoma — In clinical trials, Cymbalta was associated with an increased risk of mydriasis; therefore, it should be used cautiously in patients with controlled narrow-angle glaucoma [see Contraindications (4.2)].

Glycemic Control in Patients with Diabetes — As observed in DPNP trials, Cymbalta treatment worsens glycemic control in some patients with diabetes. In three clinical trials of Cymbalta for the management of neuropathic pain associated with diabetic peripheral neuropathy, the mean duration of diabetes was approximately 12 years, the mean baseline fasting blood glucose was 176 mg/dL, and the mean baseline hemoglobin A1c (HbA1c) was 7.8%. In the 12-week acute treatment phase of these studies, Cymbalta was associated with a small increase in mean fasting blood glucose as compared to placebo. In the extension phase of these studies, which lasted up to 52 weeks, mean fasting blood glucose increased by 12 mg/dL in the Cymbalta group and decreased by 11.5 mg/dL in the routine care group. HbA1c increased by 0.5% in the Cymbalta and by 0.2% in the routine care groups.

5.14 Urinary Hesitation and Retention

Cymbalta is in a class of drugs known to affect urethral resistance. If symptoms of urinary hesitation develop during treatment with Cymbalta, consideration should be given to the possibility that they might be drug-related.

In post marketing experience, cases of urinary retention have been observed. In some instances of urinary retention associated with duloxetine use, hospitalization and/or catheterization has been needed.

5.15 Laboratory Tests

No specific laboratory tests are recommended.

6 ADVERSE REACTIONS

6.1 Clinical Trial Data Sources

The data described below reflect exposure to duloxetine in placebo-controlled trials for MDD (N=3779), GAD (N=1018), OA (N=503), CLBP (N=600), DPNP (N=906), and FM (N=1294). The population studied was 17 to 89 years of age; 65.7%, 60.8%, 60.6%, 42.9%, and 94.4% female; and 81.8%, 72.6%, 85.3%, 74.0%, and 85.7% Caucasian for MDD, GAD, OA and CLBP, DPNP, and FM, respectively. Most patients received doses of a total of 60 to 120 mg per day [see Clinical Studies (14)].

The stated frequencies of adverse reactions represent the proportion of individuals who experienced, at least once, a treatment-emergent adverse reaction of the type listed. A reaction was considered treatment-emergent if it occurred for the first time or worsened while receiving therapy following baseline evaluation. Reactions reported during the studies were not necessarily caused by the therapy, and the frequencies do not reflect investigator impression (assessment) of causality.

Because clinical trials are conducted under widely varying conditions, adverse reaction rates observed in the clinical trials of a drug cannot be directly compared to rates in the clinical trials of another drug and may not reflect the rates observed in practice.

6.2 Adverse Reactions Reported as Reasons for Discontinuation of Treatment in Placebo-Controlled Trials

Major Depressive Disorder — Approximately 8.4% (319/3779) of the patients who received duloxetine in placebo-controlled trials for MDD discontinued treatment due to an adverse reaction, compared with 4.6% (117/2536) of the patients receiving placebo. Nausea (duloxetine 1.1%, placebo 0.4%) was the only common adverse reaction reported as a reason for discontinuation and considered to be drug-related (i.e., discontinuation occurring in at least 1% of the duloxetine-treated patients and at a rate of at least twice that of placebo).

Generalized Anxiety Disorder — Approximately 13.7% (139/1018) of the patients who received duloxetine in placebo-controlled trials for GAD discontinued treatment due to an adverse reaction, compared with 5.0% (38/767) for placebo. Common adverse reactions reported as a reason for discontinuation and considered to be drug-related (as defined above) included nausea (duloxetine 3.3%, placebo 0.4%), and dizziness (duloxetine 1.3%, placebo 0.4%).

Diabetic Peripheral Neuropathic Pain — Approximately 12.9% (117/906) of the patients who received duloxetine in placebo-controlled trials for DPNP discontinued treatment due to an adverse reaction, compared with 5.1% (23/448) for placebo. Common adverse reactions reported as a reason for discontinuation and considered to be drug-related (as defined above) included nausea (duloxetine 3.5%, placebo 0.7%), dizziness (duloxetine 1.2%, placebo 0.4%), and somnolence (duloxetine 1.1%, placebo 0.0%).

Fibromyalgia — Approximately 17.5% (227/1294) of the patients who received duloxetine in 3 to 6 month placebo-controlled trials for FM discontinued treatment due to an adverse reaction, compared with 10.1% (96/955) for placebo. Common adverse reactions reported as a reason for discontinuation and considered to be drug-related (as defined above) included nausea (duloxetine 2.0%, placebo 0.5%), headache (duloxetine 1.2%, placebo 0.3%), somnolence (duloxetine 1.1%, placebo 0.0%), and fatigue (duloxetine 1.1%, placebo 0.1%).

Chronic Pain due to Osteoarthritis — Approximately 15.7% (79/503) of the patients who received duloxetine in 13-week, placebo-controlled trials for chronic pain due to OA discontinued treatment due to an adverse reaction, compared with 7.3% (37/508) for placebo. Common adverse reactions reported as a reason for discontinuation and considered to be drug-related (as defined above) included nausea (duloxetine 2.2%, placebo 1.0%).

Chronic Low Back Pain — Approximately 16.5% (99/600) of the patients who received duloxetine in 13-week, placebo-controlled trials for CLBP discontinued treatment due to an adverse reaction, compared with 6.3% (28/441) for placebo. Common adverse reactions reported as a reason for discontinuation and considered to be drug-related (as defined above) included nausea (duloxetine 3.0%, placebo 0.7%), and somnolence (duloxetine 1.0%, placebo 0.0%).

6.3 Most Common Adverse Reactions

Pooled Trials for all Approved Indications — The most commonly observed adverse reactions in Cymbalta-treated patients (incidence of at least 5% and at least twice the incidence in placebo patients) were nausea, dry mouth, somnolence, constipation, decreased appetite, and hyperhidrosis.

Diabetic Peripheral Neuropathic Pain — The most commonly observed adverse reactions in Cymbalta-treated patients (as defined above) were nausea, somnolence, decreased appetite, constipation, hyperhidrosis, and dry mouth.

Fibromyalgia — The most commonly observed adverse reactions in Cymbalta-treated patients (as defined above) were nausea, dry mouth, constipation, somnolence, decreased appetite, hyperhidrosis, and agitation.

Chronic Pain due to Osteoarthritis — The most commonly observed adverse reactions in Cymbalta-treated patients (as defined above) were nausea, fatigue, constipation, dry mouth, insomnia, somnolence, and dizziness.

Chronic Low Back Pain — The most commonly observed adverse reactions in Cymbalta-treated patients (as defined above) were nausea, dry mouth, insomnia, somnolence, constipation, dizziness, and fatigue.

6.4 Adverse Reactions Occurring at an Incidence of 5% or More Among Duloxetine-Treated Patients in Placebo-Controlled Trials

Table 2 gives the incidence of treatment-emergent adverse reactions in placebo-controlled trials for approved indications that occurred in 5% or more of patients treated with duloxetine and with an incidence greater than placebo.

Table 2: Treatment-Emergent Adverse Reactions: Incidence of 5% or More and Greater than Placebo in Placebo-Controlled Trials of Approved Indicationsa
 | Percentage of Patients Reporting Reaction
Adverse Reaction | Cymbalta (N=8100) | Placebo (N=5655)
Nauseac | 23 | 8
Headache | 14 | 12
Dry mouth | 13 | 5
Somnolencee | 10 | 3
Fatigueb,c | 9 | 5
Insomniad | 9 | 5
Constipationc | 9 | 4
Dizzinessc | 9 | 5
Diarrhea | 9 | 6
Decreased appetitec | 7 | 2
Hyperhidrosisc | 6 | 1
Abdominal painf | 5 | 4
a The inclusion of an event in the table is determined based on the percentages before rounding; however, the percentages displayed in the table are rounded to the nearest integer.
b Also includes asthenia.
c Events for which there was a significant dose-dependent relationship in fixed-dose studies, excluding three MDD studies which did not have a placebo lead-in period or dose titration.
d Also includes initial insomnia, middle insomnia, and early morning awakening.
e Also includes hypersomnia and sedation.
f Also includes abdominal discomfort, abdominal pain lower, abdominal pain upper, abdominal tenderness, and gastrointestinal pain.

6.5 Adverse Reactions Occurring at an Incidence of 2% or More Among Duloxetine-Treated Patients in Placebo-Controlled Trials

Pooled MDD and GAD Trials — Table 3 gives the incidence of treatment-emergent adverse reactions in MDD and GAD placebo-controlled trials for approved indications that occurred in 2% or more of patients treated with duloxetine and with an incidence greater than placebo.

Table 3: Treatment-Emergent Adverse Reactions: Incidence of 2% or More and Greater than Placebo in MDD and GAD Placebo-Controlled Trialsa
 | Percentage of Patients Reporting Reaction
System Organ Class / Adverse Reaction | Cymbalta (N=4797) | Placebo (N=3303)
Cardiac Disorders
Palpitations | 2 | 1
Eye Disorders
Vision blurred | 3 | 1
Gastrointestinal Disorders
Nauseab | 23 | 8
Dry mouth | 14 | 6
Constipationb | 9 | 4
Diarrhea | 9 | 6
Abdominal painc | 5 | 4
Vomiting | 4 | 2
General Disorders and Administration Site Conditions
Fatigued | 9 | 5
Metabolism and Nutrition Disorders
Decreased appetiteb | 6 | 2
Nervous System Disorders
Headache | 14 | 14
Dizzinessb | 9 | 5
Somnolencee | 9 | 3
Tremor | 3 | 1
Psychiatric Disorders
Insomniaf | 9 | 5
Agitationg | 4 | 2
Libido decreasedh | 3 | 1
Anxiety | 3 | 2
Orgasm abnormali | 2 | <1
Reproductive System and Breast Disorders
Erectile dysfunction | 4 | 1
Ejaculation delayedb | 2 | 1
Respiratory, Thoracic, and Mediastinal Disorders
Yawning | 2 | <1
Skin and Subcutaneous Tissue Disorders
Hyperhidrosis | 6 | 2
a The inclusion of an event in the table is determined based on the percentages before rounding; however, the percentages displayed in the table are rounded to the nearest integer.
b Events for which there was a significant dose-dependent relationship in fixed-dose studies, excluding three MDD studies which did not have a placebo lead-in period or dose titration.
c Also includes abdominal pain upper, abdominal pain lower, abdominal tenderness, abdominal discomfort, and gastrointestinal pain
d Also includes asthenia
e Also includes hypersomnia and sedation
f Also includes initial insomnia, middle insomnia, and early morning awakening
g Also includes feeling jittery, nervousness, restlessness, tension and psychomotor hyperactivity
h Also includes loss of libido
i Also includes anorgasmia

DPNP, FM, OA, and CLBP — Table 4 gives the incidence of treatment-emergent adverse events that occurred in 2% or more of patients treated with Cymbalta (determined prior to rounding) in the premarketing acute phase of DPNP, FM, OA, and CLBP placebo-controlled trials and with an incidence greater than placebo.

Table 4: Treatment-Emergent Adverse Reactions: Incidence of 2% or More and Greater than Placebo in DPNP, FM, OA, and CLBP Placebo-Controlled Trialsa
System Organ Class / Adverse Reaction | Percentage of Patients Reporting Reaction
System Organ Class / Adverse Reaction | Cymbalta (N=3303) | Placebo (N=2352)
Gastrointestinal Disorders
Nausea | 23 | 7
Dry Mouthb | 11 | 3
Constipationb | 10 | 3
Diarrhea | 9 | 5
Abdominal Painc | 5 | 4
Vomiting | 3 | 2
Dyspepsia | 2 | 1
General Disorders and Administration Site Conditions
Fatigued | 11 | 5
Infections and Infestations
Nasopharyngitis | 4 | 4
Upper Respiratory Tract Infection | 3 | 3
Influenza | 2 | 2
Metabolism and Nutrition Disorders
Decreased Appetiteb | 8 | 1
Musculoskeletal and Connective Tissue Musculoskeletal Paine | 3 | 3
Muscle Spasms | 2 | 2
Back Pain | 3 | 3
Nervous System Disorders
Headache | 13 | 8
Somnolenceb,f | 11 | 3
Dizziness | 9 | 5
Paraesthesiag | 2 | 2
Tremorb | 2 | <1
Psychiatric Disorders
Insomniab,h | 10 | 5
Agitationi | 3 | <1
Reproductive System and Breast Disorders
Erectile Dysfunctionb | 4 | <1
Ejaculation Disorderj | 2 | <1
Respiratory, Thoracic, and Mediastinal Disorders
Cough | 2 | 2
Oropharyngeal Painb | 2 | 2
Skin and Subcutaneous Tissue Disorders
Hyperhidrosis | 6 | 1
Vascular Disorders
Flushingk | 3 | <1
Blood pressure increasedl | 2 | 1
a The inclusion of an event in the table is determined based on the percentages before rounding; however, the percentages displayed in the table are rounded to the nearest integer.
b Incidence of 120 mg/day is significantly greater than the incidence for 60 mg/day.
c Also includes abdominal discomfort, abdominal pain lower, abdominal pain upper, abdominal tenderness and gastrointestinal pain
d Also includes asthenia
e Also includes myalgia and neck pain
f Also includes hypersomnia and sedation
g Also includes hypoaesthesia, hypoaesthesia facial, genital hypoaesthesia and paraesthesia oral
h Also includes middle insomnia, early morning awakening and initial insomnia
i Also includes feeling jittery, nervousness, restlessness, tension and psychomotor hyperactivity
j Also includes ejaculation failure
k Also includes hot flush
l Also includes blood pressure diastolic increased, blood pressure systolic increased, diastolic hypertension, essential hypertension, hypertension, hypertensive crisis, labile hypertension, orthostatic hypertension, secondary hypertension, and systolic hypertension

6.6 Effects on Male and Female Sexual Function

Changes in sexual desire, sexual performance and sexual satisfaction often occur as manifestations of psychiatric disorders or diabetes, but they may also be a consequence of pharmacologic treatment. Because adverse sexual reactions are presumed to be voluntarily underreported, the Arizona Sexual Experience Scale (ASEX), a validated measure designed to identify sexual side effects, was used prospectively in 4 MDD placebo-controlled trials. In these trials, as shown in Table 5 below, patients treated with Cymbalta experienced significantly more sexual dysfunction, as measured by the total score on the ASEX, than did patients treated with placebo. Gender analysis showed that this difference occurred only in males. Males treated with Cymbalta experienced more difficulty with ability to reach orgasm (ASEX Item 4) than males treated with placebo. Females did not experience more sexual dysfunction on Cymbalta than on placebo as measured by ASEX total score. Negative numbers signify an improvement from a baseline level of dysfunction, which is commonly seen in depressed patients. Physicians should routinely inquire about possible sexual side effects.

Table 5: Mean Change in ASEX Scores by Gender in MDD Placebo-Controlled Trials
 | Male Patientsa |  | Female Patientsa
 | Cymbalta (n=175) | Placebo (n=83) | Cymbalta (n=241) | Placebo (n=126)
ASEX Total (Items 1-5) | 0.56b | -1.07 | -1.15 | -1.07
Item 1 — Sex drive | -0.07 | -0.12 | -0.32 | -0.24
Item 2 — Arousal | 0.01 | -0.26 | -0.21 | -0.18
Item 3 — Ability to achieve erection (men); Lubrication (women) | 0.03 | -0.25 | -0.17 | -0.18
Item 4 — Ease of reaching orgasm | 0.40c | -0.24 | -0.09 | -0.13
Item 5 — Orgasm satisfaction | 0.09 | -0.13 | -0.11 | -0.17
a n=Number of patients with non-missing change score for ASEX total
b p=0.013 versus placebo
c p<0.001 versus placebo

6.7 Vital Sign Changes

In placebo-controlled clinical trials across approved indications for change from baseline to endpoint, duloxetine treatment was associated with mean increases of 0.23 mm Hg in systolic blood pressure and 0.73 mm Hg in diastolic blood pressure compared to mean decreases of 1.09 mm Hg systolic and 0.55 mm Hg diastolic in placebo-treated patients. There was no significant difference in the frequency of sustained (3 consecutive visits) elevated blood pressure [see Warnings and Precautions (5.3 and 5.10)].

Duloxetine treatment, for up to 26 weeks in placebo-controlled trials across approved indications, typically caused a small increase in heart rate for change from baseline to endpoint compared to placebo of up to 1.37 beats per minute (increase of 1.20 beats per minute in duloxetine-treated patients, decrease of 0.17 beats per minute in placebo-treated patients).

6.8 Weight Changes

In placebo-controlled clinical trials, MDD and GAD patients treated with Cymbalta for up to 10 weeks experienced a mean weight loss of approximately 0.5 kg, compared with a mean weight gain of approximately 0.2 kg in placebo-treated patients. In studies of DPNP, FM, OA, and CLBP, patients treated with Cymbalta for up to 26 weeks experienced a mean weight loss of approximately 0.6 kg compared with a mean weight gain of approximately 0.2 kg in placebo-treated patients. In one long-term fibromyalgia 60-week uncontrolled study, duloxetine patients had a mean weight increase of 0.7 kg. In one long-term CLBP 54-week study (13-week, placebo-controlled acute phase and 41-week, uncontrolled extension phase), duloxetine patients had a mean weight decrease of 0.6 kg in 13 weeks of acute phase compared to study entry, then a mean weight increase of 1.4 kg in 41 weeks of extension phase compared to end of acute phase.

6.9 Laboratory Changes

Cymbalta treatment in placebo-controlled clinical trials across approved indications, was associated with small mean increases from baseline to endpoint in ALT, AST, CPK, alkaline phosphatase; infrequent, modest, transient, abnormal values were observed for these analytes in Cymbalta-treated patients when compared with placebo-treated patients [see Warnings and Precautions (5.2)]. High bicarbonate and cholesterol and abnormal (high or low) potassium were observed more frequently in duloxetine treated patients compared to placebo.

6.10 Electrocardiogram Changes

The effect of duloxetine 160 mg and 200 mg administered twice daily to steady state was evaluated in a randomized, double-blinded, two-way crossover study in 117 healthy female subjects. No QT interval prolongation was detected. Duloxetine appears to be associated with concentration-dependent but not clinically meaningful QT shortening.

6.11 Other Adverse Reactions Observed During the Premarketing and Postmarketing Clinical Trial Evaluation of Duloxetine

Following is a list of treatment-emergent adverse reactions reported by patients treated with duloxetine in clinical trials. In clinical trials of all indications, 34,756 patients were treated with duloxetine. Of these, 26.9% (9337) took duloxetine for at least 6 months, and 12.4% (4317) for at least one year. The following listing is not intended to include reactions (1) already listed in previous tables or elsewhere in labeling, (2) for which a drug cause was remote, (3) which were so general as to be uninformative, (4) which were not considered to have significant clinical implications, or (5) which occurred at a rate equal to or less than placebo.

Reactions are categorized by body system according to the following definitions: frequent adverse reactions are those occurring in at least 1/100 patients; infrequent adverse reactions are those occurring in 1/100 to 1/1000 patients; rare reactions are those occurring in fewer than 1/1000 patients.

Cardiac Disorders — Frequent: palpitations; Infrequent: myocardial infarction and tachycardia.

Ear and Labyrinth Disorders — Frequent: vertigo; Infrequent: ear pain and tinnitus.

Endocrine Disorders — Infrequent: hypothyroidism.

Eye Disorders — Frequent: vision blurred; Infrequent: diplopia, dry eye, and visual impairment.

Gastrointestinal Disorders — Frequent: flatulence; Infrequent: dysphagia, eructation, gastritis, gastrointestinal hemorrhage, halitosis, and stomatitis; Rare: gastric ulcer.

General Disorders and Administration Site Conditions — Frequent: chills/rigors; Infrequent: falls, feeling abnormal, feeling hot and/or cold, malaise, and thirst; Rare: gait disturbance.

Infections and Infestations — Infrequent: gastroenteritis and laryngitis.

Investigations — Frequent: weight increased, weight decreased; Infrequent: blood cholesterol increased.

Metabolism and Nutrition Disorders — Infrequent: dehydration and hyperlipidemia; Rare: dyslipidemia.

Musculoskeletal and Connective Tissue Disorders — Frequent: musculoskeletal pain; Infrequent: muscle tightness and muscle twitching.

Nervous System Disorders — Frequent: dysgeusia, lethargy, and parasthesia/hypoesthesia; Infrequent: disturbance in attention, dyskinesia, myoclonus, and poor quality sleep; Rare: dysarthria.

Psychiatric Disorders — Frequent: abnormal dreams and sleep disorder; Infrequent: apathy, bruxism, disorientation/confusional state, irritability, mood swings, and suicide attempt; Rare: completed suicide.

Renal and Urinary Disorders — Frequent: urinary frequency; Infrequent: dysuria, micturition urgency, nocturia, polyuria, and urine odor abnormal.

Reproductive System and Breast Disorders — Frequent: anorgasmia/orgasm abnormal; Infrequent: menopausal symptoms, sexual dysfunction, and testicular pain; Rare: menstrual disorder.

Respiratory, Thoracic and Mediastinal Disorders — Frequent: yawning, oropharyngeal pain; Infrequent: throat tightness.

Skin and Subcutaneous Tissue Disorders — Frequent: pruritus; Infrequent: cold sweat, dermatitis contact, erythema, increased tendency to bruise, night sweats, and photosensitivity reaction; Rare: ecchymosis.

Vascular Disorders — Frequent: hot flush; Infrequent: flushing, orthostatic hypotension, and peripheral coldness.

6.12 Postmarketing Spontaneous Reports

The following adverse reactions have been identified during postapproval use of Cymbalta. Because these reactions are reported voluntarily from a population of uncertain size, it is not always possible to reliably estimate their frequency or establish a causal relationship to drug exposure.

Adverse reactions reported since market introduction that were temporally related to duloxetine therapy and not mentioned elsewhere in labeling include: anaphylactic reaction, aggression and anger (particularly early in treatment or after treatment discontinuation), angioneurotic edema, extrapyramidal disorder, galactorrhea, glaucoma, gynecological bleeding, hallucinations, hyperglycemia, hyperprolactinemia, hypersensitivity, hypertensive crisis, muscle spasm, rash, restless legs syndrome, seizures upon treatment discontinuation, supraventricular arrhythmia, tinnitus (upon treatment discontinuation), trismus, and urticaria.

7 DRUG INTERACTIONS

Both CYP1A2 and CYP2D6 are responsible for duloxetine metabolism.

7.1 Inhibitors of CYP1A2

When duloxetine 60 mg was co-administered with fluvoxamine 100 mg, a potent CYP1A2 inhibitor, to male subjects (n=14) duloxetine AUC was increased approximately 6-fold, the Cmax was increased about 2.5-fold, and duloxetine t1/2 was increased approximately 3-fold. Other drugs that inhibit CYP1A2 metabolism include cimetidine and quinolone antimicrobials such as ciprofloxacin and enoxacin [see Warnings and Precautions (5.11)].

7.2 Inhibitors of CYP2D6

Concomitant use of duloxetine (40 mg once daily) with paroxetine (20 mg once daily) increased the concentration of duloxetine AUC by about 60%, and greater degrees of inhibition are expected with higher doses of paroxetine. Similar effects would be expected with other potent CYP2D6 inhibitors (e.g., fluoxetine, quinidine) [see Warnings and Precautions (5.11)].

7.3 Dual Inhibition of CYP1A2 and CYP2D6

Concomitant administration of duloxetine 40 mg twice daily with fluvoxamine 100 mg, a potent CYP1A2 inhibitor, to CYP2D6 poor metabolizer subjects (n=14) resulted in a 6-fold increase in duloxetine AUC and Cmax.

7.4 Drugs that Interfere with Hemostasis (e.g., NSAIDs, Aspirin, and Warfarin)

Serotonin release by platelets plays an important role in hemostasis. Epidemiological studies of the case-control and cohort design that have demonstrated an association between use of psychotropic drugs that interfere with serotonin reuptake and the occurrence of upper gastrointestinal bleeding have also shown that concurrent use of an NSAID or aspirin may potentiate this risk of bleeding. Altered anticoagulant effects, including increased bleeding, have been reported when SSRIs or SNRIs are co-administered with warfarin. Concomitant administration of warfarin (2-9 mg once daily) under steady state conditions with duloxetine 60 or 120 mg once daily for up to 14 days in healthy subjects (n=15) did not significantly change INR from baseline (mean INR changes ranged from 0.05 to +0.07). The total warfarin (protein bound plus free drug) pharmacokinetics (AUCτ,ss, Cmax,ss or tmax,ss) for both R- and S-warfarin were not altered by duloxetine. Because of the potential effect of duloxetine on platelets, patients receiving warfarin therapy should be carefully monitored when duloxetine is initiated or discontinued [see Warnings and Precautions (5.5)].

7.5 Lorazepam

Under steady-state conditions for duloxetine (60 mg Q 12 hours) and lorazepam (2 mg Q 12 hours), the pharmacokinetics of duloxetine were not affected by co-administration.

7.6 Temazepam

Under steady-state conditions for duloxetine (20 mg qhs) and temazepam (30 mg qhs), the pharmacokinetics of duloxetine were not affected by co-administration.

7.7 Drugs that Affect Gastric Acidity

Cymbalta has an enteric coating that resists dissolution until reaching a segment of the gastrointestinal tract where the pH exceeds 5.5. In extremely acidic conditions, Cymbalta, unprotected by the enteric coating, may undergo hydrolysis to form naphthol. Caution is advised in using Cymbalta in patients with conditions that may slow gastric emptying (e.g., some diabetics). Drugs that raise the gastrointestinal pH may lead to an earlier release of duloxetine. However, co-administration of Cymbalta with aluminum- and magnesium-containing antacids (51 mEq) or Cymbalta with famotidine, had no significant effect on the rate or extent of duloxetine absorption after administration of a 40 mg oral dose. It is unknown whether the concomitant administration of proton pump inhibitors affects duloxetine absorption [see Warnings and Precautions (5.13)].

7.8 Drugs Metabolized by CYP1A2

In vitro drug interaction studies demonstrate that duloxetine does not induce CYP1A2 activity. Therefore, an increase in the metabolism of CYP1A2 substrates (e.g., theophylline, caffeine) resulting from induction is not anticipated, although clinical studies of induction have not been performed. Duloxetine is an inhibitor of the CYP1A2 isoform in in vitro studies, and in two clinical studies the average (90% confidence interval) increase in theophylline AUC was 7% (1%-15%) and 20% (13%-27%) when co-administered with duloxetine (60 mg twice daily).

7.9 Drugs Metabolized by CYP2D6

Duloxetine is a moderate inhibitor of CYP2D6. When duloxetine was administered (at a dose of 60 mg twice daily) in conjunction with a single 50 mg dose of desipramine, a CYP2D6 substrate, the AUC of desipramine increased 3-fold [see Warnings and Precautions (5.11)].

7.10 Drugs Metabolized by CYP2C9

Results of in vitro studies demonstrate that duloxetine does not inhibit activity. In a clinical study, the pharmacokinetics of S-warfarin, a CYP2C9 substrate, were not significantly affected by duloxetine [see Drug Interactions (7.4)].

7.11 Drugs Metabolized by CYP3A

Results of in vitro studies demonstrate that duloxetine does not inhibit or induce CYP3A activity. Therefore, an increase or decrease in the metabolism of CYP3A substrates (e.g., oral contraceptives and other steroidal agents) resulting from induction or inhibition is not anticipated, although clinical studies have not been performed.

7.12 Drugs Metabolized by CYP2C19

Results of in vitro studies demonstrate that duloxetine does not inhibit CYP2C19 activity at therapeutic concentrations. Inhibition of the metabolism of CYP2C19 substrates is therefore not anticipated, although clinical studies have not been performed.

7.13 Monoamine Oxidase Inhibitors (MAOIs)

[See Dosage and Administration (2.5, 2.6), Contraindications (4.1), and Warnings and Precautions (5.4)].

7.14 Serotonergic Drugs

[See Dosage and Administration (2.5, 2.6), Contraindications (4.1), and Warnings and Precautions (5.4)].

7.15 Alcohol

When Cymbalta and ethanol were administered several hours apart so that peak concentrations of each would coincide, Cymbalta did not increase the impairment of mental and motor skills caused by alcohol.

In the Cymbalta clinical trials database, three Cymbalta-treated patients had liver injury as manifested by ALT and total bilirubin elevations, with evidence of obstruction. Substantial intercurrent ethanol use was present in each of these cases, and this may have contributed to the abnormalities seen [see Warnings and Precautions (5.2 and 5.11)].

7.16 CNS Drugs

[See Warnings and Precautions (5.11)].

7.17 Drugs Highly Bound to Plasma Protein

Because duloxetine is highly bound to plasma protein, administration of Cymbalta to a patient taking another drug that is highly protein bound may cause increased free concentrations of the other drug, potentially resulting in adverse reactions. However, co-administration of duloxetine (60 or 120 mg) with warfarin (2-9 mg), a highly protein-bound drug, did not result in significant changes in INR and in the pharmacokinetics of either total S-or total R-warfarin (protein bound plus free drug) [see Drug Interactions (7.4)].

8 USE IN SPECIFIC POPULATIONS

8.1 Pregnancy

TERATOGENIC EFFECTS

Teratogenic Effects, Pregnancy Category C — In animal reproduction studies, duloxetine has been shown to have adverse effects on embryo/fetal and postnatal development.

When duloxetine was administered orally to pregnant rats and rabbits during the period of organogenesis, there was no evidence of teratogenicity at doses up to 45 mg/kg/day (7 times the maximum recommended human dose [MRHD, 60 mg/day] and 4 times the human dose of 120 mg/day on a mg/m^2 basis, in rat; 15 times the MRHD and 7 times the human dose of 120 mg/day on a mg/m^2 basis in rabbit). However, fetal weights were decreased at this dose, with a no-effect dose of 10 mg/kg/day (2 times the MRHD and ≈1 times the human dose of 120 mg/day on a mg/m^2 basis in rats; 3 times the MRHD and 2 times the human dose of 120 mg/day on a mg/m^2 basis in rabbits).

When duloxetine was administered orally to pregnant rats throughout gestation and lactation, the survival of pups to 1 day postpartum and pup body weights at birth and during the lactation period were decreased at a dose of 30 mg/kg/day (5 times the MRHD and 2 times the human dose of 120 mg/day on a mg/m^2 basis); the no-effect dose was 10 mg/kg/day. Furthermore, behaviors consistent with increased reactivity, such as increased startle response to noise and decreased habituation of locomotor activity, were observed in pups following maternal exposure to 30 mg/kg/day. Post-weaning growth and reproductive performance of the progeny were not affected adversely by maternal duloxetine treatment.

There are no adequate and well-controlled studies in pregnant women; therefore, duloxetine should be used during pregnancy only if the potential benefit justifies the potential risk to the fetus.

NONTERATOGENIC EFFECTS

Nonteratogenic Effects — Neonates exposed to SSRIs or serotonin and norepinephrine reuptake inhibitors (SNRIs), late in the third trimester have developed complications requiring prolonged hospitalization, respiratory support, and tube feeding. Such complications can arise immediately upon delivery. Reported clinical findings have included respiratory distress, cyanosis, apnea, seizures, temperature instability, feeding difficulty, vomiting, hypoglycemia, hypotonia, hypertonia, hyperreflexia, tremor, jitteriness, irritability, and constant crying. These features are consistent with either a direct toxic effect of SSRIs and SNRIs or, possibly, a drug discontinuation syndrome. It should be noted that, in some cases, the clinical picture is consistent with serotonin syndrome [see Warnings and Precautions (5.4)].

When treating pregnant women with Cymbalta during the third trimester, the physician should carefully consider the potential risks and benefits of treatment. The physician may consider tapering Cymbalta in the third trimester [see Dosage and Administration (2.3)].

Lilly maintains a pregnancy registry to monitor the pregnancy outcomes of women exposed to Cymbalta while pregnant. Healthcare providers are encouraged to register any patient who is exposed to Cymbalta during pregnancy by calling the Cymbalta Pregnancy Registry at 1-866-814-6975 or by visiting www.cymbaltapregnancyregistry.com

8.2 Labor and Delivery

The effect of duloxetine on labor and delivery in humans is unknown. Duloxetine should be used during labor and delivery only if the potential benefit justifies the potential risk to the fetus.

8.3 Nursing Mothers

Duloxetine is excreted into the milk of lactating women. The estimated daily infant dose on a mg/kg basis is approximately 0.14% of the maternal dose. Because the safety of duloxetine in infants is not known, nursing while on Cymbalta is not recommended. However, if the physician determines that the benefit of duloxetine therapy for the mother outweighs any potential risk to the infant, no dosage adjustment is required as lactation did not influence duloxetine pharmacokinetics.

The disposition of duloxetine was studied in 6 lactating women who were at least 12 weeks postpartum. Duloxetine 40 mg twice daily was given for 3.5 days. Like many other drugs, duloxetine is detected in breast milk, and steady state concentrations in breast milk are about one-fourth those in plasma. The amount of duloxetine in breast milk is approximately 7 μg/day while on 40 mg BID dosing. The excretion of duloxetine metabolites into breast milk was not examined. Because the safety of duloxetine in infants is not known, nursing while on Cymbalta is not recommended [see Dosage and Administration (2.3)].

8.4 Pediatric Use

Efficacy was not demonstrated in two 10-week, placebo-controlled trials with 800 pediatric patients with MDD, age 7-17. Neither Cymbalta nor the active control (indicated for treatment of pediatric depression) statistically separated from placebo. Duloxetine steady state plasma concentration was comparable in children (7 - 12 years), adolescents (13 - 17 years) and adults. Cymbalta has not been studied in patients under the age of 7. Thus, safety and effectiveness in the pediatric population has not been established [see Boxed Warning and Warnings and Precautions (5.1)].

Decreased appetite and weight loss have been observed in association with the use of SSRIs and SNRIs. Pediatric patients treated with Cymbalta in MDD clinical trials experienced a 0.2 kg mean decrease in weight at 10-weeks, compared with a mean weight gain of approximately 0.6 kg in placebo-treated patients. The proportion of patients who experienced a clinically significant decrease in weight (≥3.5%) was greater in the Cymbalta group than in the placebo group (11% and 6%, respectively). Subsequently, over the six-month uncontrolled extension period, most Cymbalta-treated patients trended toward recovery to their expected baseline weight percentile based on population data from age- and gender-matched peers. Perform regular monitoring of weight and growth in children and adolescents treated with an SNRI such as Cymbalta.

In the 2 pediatric MDD studies, the safety findings were consistent with the known safety and tolerability profile for Cymbalta.

Duloxetine administration to young rats from post-natal day 21 (weaning) through post-natal day 90 (adult) resulted in decreased body weights that persisted into adulthood, but recovered when drug treatment was discontinued; slightly delayed (~1.5 days) sexual maturation in females, without any effect on fertility; and a delay in learning a complex task in adulthood, which was not observed after drug treatment was discontinued. These effects were observed at the high dose of 45 mg/kg/day; the no-effect-level was 20 mg/kg/day.

8.5 Geriatric Use

Of the 2,418 patients in premarketing clinical studies of Cymbalta for MDD, 5.9% (143) were 65 years of age or over. Of the 1041 patients in CLBP premarketing studies, 21.2% (221) were 65 years of age or over. Of the 487 patients in OA premarketing studies, 40.5% (197) were 65 years of age or over. Of the 1,074 patients in the DPNP premarketing studies, 33% (357) were 65 years of age or over. Of the 1,761 patients in FM premarketing studies, 7.9% (140) were 65 years of age or over. Premarketing clinical studies of GAD did not include sufficient numbers of subjects age 65 or over to determine whether they respond differently from younger subjects. In the MDD, DPNP, FM, OA, and CLBP studies, no overall differences in safety or effectiveness were generally observed between these subjects and younger subjects, and other reported clinical experience has not identified differences in responses between the elderly and younger patients, but greater sensitivity of some older individuals cannot be ruled out. SSRIs and SNRIs, including Cymbalta have been associated with cases of clinically significant hyponatremia in elderly patients, who may be at greater risk for this adverse event [see Warnings and Precautions (5.12)]. In a subgroup analysis of patients 65 years of age and older (N=3278) from all placebo-controlled trials, 1.1% of patients treated with duloxetine reported one or more falls, compared with 0.4% of patients treated with placebo. While many patients with falls had underlying potential risk factors for falls (e.g., medications; medical comorbidities; gait disturbances), the impact of these factors on falls is unclear. Fall with serious consequences including bone fractures and hospitalizations have been reported [see Other Adverse Reactions Observed During the Premarketing and Postmarketing Clinical Trial Evaluation of Duloxetine (6.11)].

The pharmacokinetics of duloxetine after a single dose of 40 mg were compared in healthy elderly females (65 to 77 years) and healthy middle-age females (32 to 50 years). There was no difference in the Cmax, but the AUC of duloxetine was somewhat (about 25%) higher and the half-life about 4 hours longer in the elderly females. Population pharmacokinetic analyses suggest that the typical values for clearance decrease by approximately 1% for each year of age between 25 to 75 years of age; but age as a predictive factor only accounts for a small percentage of between-patient variability. Dosage adjustment based on the age of the patient is not necessary [see Dosage and Administration (2.3)].

8.6 Gender

Duloxetine's half-life is similar in men and women. Dosage adjustment based on gender is not necessary.

8.7 Smoking Status

Duloxetine bioavailability (AUC) appears to be reduced by about one-third in smokers. Dosage modifications are not recommended for smokers.

8.8 Race

No specific pharmacokinetic study was conducted to investigate the effects of race.

8.9 Hepatic Insufficiency

Patients with clinically evident hepatic insufficiency have decreased duloxetine metabolism and elimination. After a single 20 mg dose of Cymbalta, 6 cirrhotic patients with moderate liver impairment (Child-Pugh Class B) had a mean plasma duloxetine clearance about 15% that of age- and gender-matched healthy subjects, with a 5-fold increase in mean exposure (AUC). Although Cmax was similar to normals in the cirrhotic patients, the half-life was about 3 times longer [see Dosage and Administration (2.3) and Warnings and Precautions (5.13)].

8.10 Severe Renal Impairment

Limited data are available on the effects of duloxetine in patients with end-stage renal disease (ESRD). After a single 60 mg dose of duloxetine, Cmax and AUC values were approximately 100% greater in patients with end-stage renal disease receiving chronic intermittent hemodialysis than in subjects with normal renal function. The elimination half-life, however, was similar in both groups. The AUCs of the major circulating metabolites, 4-hydroxy duloxetine glucuronide and 5-hydroxy, 6-methoxy duloxetine sulfate, largely excreted in urine, were approximately 7- to 9-fold higher and would be expected to increase further with multiple dosing. Population PK analyses suggest that mild to moderate degrees of renal dysfunction (estimated CrCl 30-80 mL/min) have no significant effect on duloxetine apparent clearance [see Dosage and Administration (2.3) and Warnings and Precautions (5.13)].

9 DRUG ABUSE AND DEPENDENCE

9.2 Abuse

In animal studies, duloxetine did not demonstrate barbiturate-like (depressant) abuse potential.

While Cymbalta has not been systematically studied in humans for its potential for abuse, there was no indication of drug-seeking behavior in the clinical trials. However, it is not possible to predict on the basis of premarketing experience the extent to which a CNS active drug will be misused, diverted, and/or abused once marketed. Consequently, physicians should carefully evaluate patients for a history of drug abuse and follow such patients closely, observing them for signs of misuse or abuse of Cymbalta (e.g., development of tolerance, incrementation of dose, drug-seeking behavior).

9.3 Dependence

In drug dependence studies, duloxetine did not demonstrate dependence-producing potential in rats.

10 OVERDOSAGE

10.1 Signs and Symptoms

In postmarketing experience, fatal outcomes have been reported for acute overdoses, primarily with mixed overdoses, but also with duloxetine only, at doses as low as 1000 mg. Signs and symptoms of overdose (duloxetine alone or with mixed drugs) included somnolence, coma, serotonin syndrome, seizures, syncope, tachycardia, hypotension, hypertension, and vomiting.

10.2 Management of Overdose

There is no specific antidote to Cymbalta, but if serotonin syndrome ensues, specific treatment (such as with cyproheptadine and/or temperature control) may be considered. In case of acute overdose, treatment should consist of those general measures employed in the management of overdose with any drug.

An adequate airway, oxygenation, and ventilation should be assured, and cardiac rhythm and vital signs should be monitored. Induction of emesis is not recommended. Gastric lavage with a large-bore orogastric tube with appropriate airway protection, if needed, may be indicated if performed soon after ingestion or in symptomatic patients.

Activated charcoal may be useful in limiting absorption of duloxetine from the gastrointestinal tract. Administration of activated charcoal has been shown to decrease AUC and Cmax by an average of one-third, although some subjects had a limited effect of activated charcoal. Due to the large volume of distribution of this drug, forced diuresis, dialysis, hemoperfusion, and exchange transfusion are unlikely to be beneficial.

In managing overdose, the possibility of multiple drug involvement should be considered. A specific caution involves patients who are taking or have recently taken Cymbalta and might ingest excessive quantities of a TCA. In such a case, decreased clearance of the parent tricyclic and/or its active metabolite may increase the possibility of clinically significant sequelae and extend the time needed for close medical observation [see Warnings and Precautions (5.4) and Drug Interactions (7)]. The physician should consider contacting a poison control center for additional information on the treatment of any overdose. Telephone numbers for certified poison control centers are listed in the Physicians' Desk Reference (PDR).

11 DESCRIPTION

Cymbalta® (Duloxetine Delayed-Release Capsules) is a selective serotonin and norepinephrine reuptake inhibitor (SSNRI) for oral administration. Its chemical designation is (+)-(S)-N-methyl-γ-(1-naphthyloxy)-2-thiophenepropylamine hydrochloride. The empirical formula is C18H19NOS•HCl, which corresponds to a molecular weight of 333.88. The structural formula is:

Duloxetine hydrochloride is a white to slightly brownish white solid, which is slightly soluble in water.

Each capsule contains enteric-coated pellets of 22.4, 33.7, or 67.3 mg of duloxetine hydrochloride equivalent to 20, 30, or 60 mg of duloxetine, respectively. These enteric-coated pellets are designed to prevent degradation of the drug in the acidic environment of the stomach. Inactive ingredients include FD&C Blue No. 2, gelatin, hypromellose, hydroxypropyl methylcellulose acetate succinate, sodium lauryl sulfate, sucrose, sugar spheres, talc, titanium dioxide, and triethyl citrate. The 20 and 60 mg capsules also contain iron oxide yellow.

12 CLINICAL PHARMACOLOGY

12.1 Mechanism of Action

Although the exact mechanisms of the antidepressant, central pain inhibitory and anxiolytic actions of duloxetine in humans are unknown, these actions are believed to be related to its potentiation of serotonergic and noradrenergic activity in the CNS.

12.2 Pharmacodynamics

Preclinical studies have shown that duloxetine is a potent inhibitor of neuronal serotonin and norepinephrine reuptake and a less potent inhibitor of dopamine reuptake. Duloxetine has no significant affinity for dopaminergic, adrenergic, cholinergic, histaminergic, opioid, glutamate, and GABA receptors in vitro. Duloxetine does not inhibit monoamine oxidase (MAO).

Cymbalta is in a class of drugs known to affect urethral resistance. If symptoms of urinary hesitation develop during treatment with Cymbalta, consideration should be given to the possibility that they might be drug-related.

12.3 Pharmacokinetics

Duloxetine has an elimination half-life of about 12 hours (range 8 to 17 hours) and its pharmacokinetics are dose proportional over the therapeutic range. Steady-state plasma concentrations are typically achieved after 3 days of dosing. Elimination of duloxetine is mainly through hepatic metabolism involving two P450 isozymes, CYP1A2 and CYP2D6.

Absorption and Distribution — Orally administered duloxetine hydrochloride is well absorbed. There is a median 2 hour lag until absorption begins (Tlag), with maximal plasma concentrations (Cmax) of duloxetine occurring 6 hours post dose. Food does not affect the Cmax of duloxetine, but delays the time to reach peak concentration from 6 to 10 hours and it marginally decreases the extent of absorption (AUC) by about 10%. There is a 3 hour delay in absorption and a one-third increase in apparent clearance of duloxetine after an evening dose as compared to a morning dose.

The apparent volume of distribution averages about 1640 L. Duloxetine is highly bound (>90%) to proteins in human plasma, binding primarily to albumin and α1-acid glycoprotein. The interaction between duloxetine and other highly protein bound drugs has not been fully evaluated. Plasma protein binding of duloxetine is not affected by renal or hepatic impairment.

Metabolism and Elimination — Biotransformation and disposition of duloxetine in humans have been determined following oral administration of ^14C-labeled duloxetine. Duloxetine comprises about 3% of the total radiolabeled material in the plasma, indicating that it undergoes extensive metabolism to numerous metabolites. The major biotransformation pathways for duloxetine involve oxidation of the naphthyl ring followed by conjugation and further oxidation. Both CYP1A2 and CYP2D6 catalyze the oxidation of the naphthyl ring in vitro. Metabolites found in plasma include 4-hydroxy duloxetine glucuronide and 5-hydroxy, 6-methoxy duloxetine sulfate. Many additional metabolites have been identified in urine, some representing only minor pathways of elimination. Only trace (<1% of the dose) amounts of unchanged duloxetine are present in the urine. Most (about 70%) of the duloxetine dose appears in the urine as metabolites of duloxetine; about 20% is excreted in the feces. Duloxetine undergoes extensive metabolism, but the major circulating metabolites have not been shown to contribute significantly to the pharmacologic activity of duloxetine.

13 NONCLINICAL TOXICOLOGY

13.1 Carcinogenesis, Mutagenesis, Impairment of Fertility

Carcinogenesis — Duloxetine was administered in the diet to mice and rats for 2 years.

In female mice receiving duloxetine at 140 mg/kg/day (11 times the maximum recommended human dose [MRHD, 60 mg/day] and 6 times the human dose of 120 mg/day on a mg/m^2 basis), there was an increased incidence of hepatocellular adenomas and carcinomas. The no-effect dose was 50 mg/kg/day (4 times the MRHD and 2 times the human dose of 120 mg/day on a mg/m^2 basis). Tumor incidence was not increased in male mice receiving duloxetine at doses up to 100 mg/kg/day (8 times the MRHD and 4 times the human dose of 120 mg/day on a mg/m^2 basis).

In rats, dietary doses of duloxetine up to 27 mg/kg/day in females (4 times the MRHD and 2 times the human dose of 120 mg/day on a mg/m^2 basis) and up to 36 mg/kg/day in males (6 times the MRHD and 3 times the human dose of 120 mg/day on a mg/m^2 basis) did not increase the incidence of tumors.

Mutagenesis — Duloxetine was not mutagenic in the in vitro bacterial reverse mutation assay (Ames test) and was not clastogenic in an in vivo chromosomal aberration test in mouse bone marrow cells. Additionally, duloxetine was not genotoxic in an in vitro mammalian forward gene mutation assay in mouse lymphoma cells or in an in vitro unscheduled DNA synthesis (UDS) assay in primary rat hepatocytes, and did not induce sister chromatid exchange in Chinese hamster bone marrow in vivo.

Impairment of Fertility — Duloxetine administered orally to either male or female rats prior to and throughout mating at doses up to 45 mg/kg/day (7 times the maximum recommended human dose of 60 mg/day and 4 times the human dose of 120 mg/day on a mg/m^2 basis) did not alter mating or fertility.

14 CLINICAL STUDIES

14.1 Major Depressive Disorder

The efficacy of Cymbalta as a treatment for depression was established in 4 randomized, double-blind, placebo-controlled, fixed-dose studies in adult outpatients (18 to 83 years) meeting DSM-IV criteria for major depression. In 2 studies, patients were randomized to Cymbalta 60 mg once daily (N=123 and N=128, respectively) or placebo (N=122 and N=139, respectively) for 9 weeks; in the third study, patients were randomized to Cymbalta 20 or 40 mg twice daily (N=86 and N=91, respectively) or placebo (N=89) for 8 weeks; in the fourth study, patients were randomized to Cymbalta 40 or 60 mg twice daily (N=95 and N=93, respectively) or placebo (N=93) for 8 weeks. There is no evidence that doses greater than 60 mg/day confer additional benefits.

In all 4 studies, Cymbalta demonstrated superiority over placebo as measured by improvement in the 17-item Hamilton Depression Rating Scale (HAMD-17) total score.

In all of these clinical studies, analyses of the relationship between treatment outcome and age, gender, and race did not suggest any differential responsiveness on the basis of these patient characteristics.

In another study, 533 patients meeting DSM-IV criteria for MDD received Cymbalta 60 mg once daily during an initial 12-week open-label treatment phase. Two hundred and seventy-eight patients who responded to open label treatment (defined as meeting the following criteria at weeks 10 and 12: a HAMD-17 total score ≤9, Clinical Global Impressions of Severity (CGI-S) ≤2, and not meeting the DSM-IV criteria for MDD) were randomly assigned to continuation of Cymbalta at the same dose (N=136) or to placebo (N=142) for 6 months. Patients on Cymbalta experienced a statistically significantly longer time to relapse of depression than did patients on placebo. Relapse was defined as an increase in the CGI-S score of ≥2 points compared with that obtained at week 12, as well as meeting the DSM-IV criteria for MDD at 2 consecutive visits at least 2 weeks apart, where the 2-week temporal criterion had to be satisfied at only the second visit. The effectiveness of Cymbalta in hospitalized patients with major depressive disorder has not been studied.

14.2 Generalized Anxiety Disorder

The efficacy of Cymbalta in the treatment of generalized anxiety disorder (GAD) was established in 1 fixed-dose randomized, double-blind, placebo-controlled trial and 2 flexible-dose randomized, double-blind, placebo-controlled trials in adult outpatients between 18 and 83 years of age meeting the DSM-IV criteria for GAD.

In 1 flexible-dose study and in the fixed-dose study, the starting dose was 60 mg once daily where down titration to 30 mg once daily was allowed for tolerability reasons before increasing it to 60 mg once daily. Fifteen percent of patients were down titrated. One flexible-dose study had a starting dose of 30 mg once daily for 1 week before increasing it to 60 mg once daily.

The 2 flexible-dose studies involved dose titration with Cymbalta doses ranging from 60 mg once daily to 120 mg once daily (N=168 and N=162) compared to placebo (N=159 and N=161) over a 10-week treatment period. The mean dose for completers at endpoint in the flexible-dose studies was 104.75 mg/day. The fixed-dose study evaluated Cymbalta doses of 60 mg once daily (N=168) and 120 mg once daily (N=170) compared to placebo (N=175) over a 9-week treatment period. While a 120 mg/day dose was shown to be effective, there is no evidence that doses greater than 60 mg/day confer additional benefit.

In all 3 studies, Cymbalta demonstrated superiority over placebo as measured by greater improvement in the Hamilton Anxiety Scale (HAM-A) total score and by the Sheehan Disability Scale (SDS) global functional impairment score. The SDS is a widely used and well-validated scale that measures the extent emotional symptoms disrupt patient functioning in 3 life domains: work/school, social life/leisure activities, and family life/home responsibilities.

In another study, 887 patients meeting DSM-IV-TR criteria for GAD received Cymbalta 60 mg to 120 mg once daily during an initial 26-week open-label treatment phase. Four hundred and twenty-nine patients who responded to open-label treatment (defined as meeting the following criteria at weeks 24 and 26: a decrease from baseline HAM-A total score by at least 50% to a score no higher than 11, and a Clinical Global Impressions of Improvement [CGI-Improvement] score of 1 or 2) were randomly assigned to continuation of Cymbalta at the same dose (N=216) or to placebo (N=213) and were observed for relapse. Of the patients randomized, 73% had been in a responder status for at least 10 weeks. Relapse was defined as an increase in CGI-Severity score at least 2 points to a score ≥4 and a MINI (Mini-International Neuropsychiatric Interview) diagnosis of GAD (excluding duration), or discontinuation due to lack of efficacy. Patients taking Cymbalta experienced a statistically significantly longer time to relapse of GAD than did patients taking placebo.

Subgroup analyses did not indicate that there were any differences in treatment outcomes as a function of age or gender.

14.3 Diabetic Peripheral Neuropathic Pain

The efficacy of Cymbalta for the management of neuropathic pain associated with diabetic peripheral neuropathy was established in 2 randomized, 12-week, double-blind, placebo-controlled, fixed-dose studies in adult patients having diabetic peripheral neuropathic pain for at least 6 months. Study DPNP-1 and Study DPNP-2 enrolled a total of 791 patients of whom 592 (75%) completed the studies. Patients enrolled had Type I or II diabetes mellitus with a diagnosis of painful distal symmetrical sensorimotor polyneuropathy for at least 6 months. The patients had a baseline pain score of ≥4 on an 11-point scale ranging from 0 (no pain) to 10 (worst possible pain). Patients were permitted up to 4 g of acetaminophen per day as needed for pain, in addition to Cymbalta. Patients recorded their pain daily in a diary.

Both studies compared Cymbalta 60 mg once daily or 60 mg twice daily with placebo. DPNP-1 additionally compared Cymbalta 20 mg with placebo. A total of 457 patients (342 Cymbalta, 115 placebo) were enrolled in DPNP-1 and a total of 334 patients (226 Cymbalta, 108 placebo) were enrolled in DPNP-2. Treatment with Cymbalta 60 mg one or two times a day statistically significantly improved the endpoint mean pain scores from baseline and increased the proportion of patients with at least a 50% reduction in pain scores from baseline. For various degrees of improvement in pain from baseline to study endpoint, Figures 1 and 2 show the fraction of patients achieving that degree of improvement. The figures are cumulative, so that patients whose change from baseline is, for example, 50%, are also included at every level of improvement below 50%. Patients who did not complete the study were assigned 0% improvement. Some patients experienced a decrease in pain as early as week 1, which persisted throughout the study.

Figure 1: Percentage of Patients Achieving Various Levels of Pain Relief as Measured by 24-Hour Average Pain Severity - DPNP-1
Figure 2: Percentage of Patients Achieving Various Levels of Pain Relief as Measured by 24-Hour Average Pain Severity - DPNP-2

14.4 Fibromyalgia

The efficacy of Cymbalta for the management of fibromyalgia was established in two randomized, double-blind, placebo-controlled, fixed-dose studies in adult patients meeting the American College of Rheumatology criteria for fibromyalgia (a history of widespread pain for 3 months, and pain present at 11 or more of the 18 specific tender point sites). Study FM-1 was three months in duration and enrolled female patients only. Study FM-2 was six months in duration and enrolled male and female patients. Approximately 25% of participants had a comorbid diagnosis of major depressive disorder (MDD). FM-1 and FM-2 enrolled a total of 874 patients of whom 541 (62%) completed the studies. The patients had a baseline pain score of 6.5 on an 11-point scale ranging from 0 (no pain) to 10 (worse possible pain).

Both studies compared Cymbalta 60 mg once daily or 120 mg daily (given in divided doses in FM-1 and as a single daily dose in FM-2) with placebo. FM-2 additionally compared Cymbalta 20 mg with placebo during the initial three months of a six-month study. A total of 354 patients (234 Cymbalta, 120 placebo) were enrolled in FM-1 and a total of 520 patients (376 Cymbalta, 144 placebo) were enrolled in FM-2 (5% male, 95% female). Treatment with Cymbalta 60 mg or 120 mg daily statistically significantly improved the endpoint mean pain scores from baseline and increased the proportion of patients with at least a 50% reduction in pain score from baseline. Pain reduction was observed in patients both with and without comorbid MDD. However, the degree of pain reduction may be greater in patients with comorbid MDD. For various degrees of improvement in pain from baseline to study endpoint, Figures 3 and 4 show the fraction of patients achieving that degree of improvement. The figures are cumulative so that patients whose change from baseline is, for example, 50%, are also included at every level of improvement below 50%. Patients who did not complete the study were assigned 0% improvement. Some patients experienced a decrease in pain as early as week 1, which persisted throughout the study. Improvement was also demonstrated on measures of function (Fibromyalgia Impact Questionnaires) and patient global impression of change (PGI). Neither study demonstrated a benefit of 120 mg compared to 60 mg, and a higher dose was associated with more adverse reactions and premature discontinuations of treatment.

Figure 3: Percentage of Patients Achieving Various Levels of Pain Relief as Measured by 24-Hour Average Pain Severity - FM-1
Figure 4: Percentage of Patients Achieving Various Levels of Pain Relief as Measured by 24-Hour Average Pain Severity - FM-2

Additionally, the benefit of up-titration in non-responders to Cymbalta at 60 mg/day was evaluated in a separate study. Patients were initially treated with Cymbalta 60 mg once daily for eight weeks in open-label fashion. Subsequently, completers of this phase were randomized to double-blind treatment with Cymbalta at either 60 mg once daily or 120 mg once daily. Those patients who were considered non-responders, where response was defined as at least a 30% reduction in pain score from baseline at the end of the 8-week treatment, were no more likely to meet response criteria at the end of 60 weeks of treatment if blindly titrated to Cymbalta 120 mg as compared to those who were blindly continued on Cymbalta 60 mg.

14.5 Chronic Musculoskeletal Pain

Cymbalta is indicated for the management of chronic musculoskeletal pain. This has been established in studies in patients with chronic low back pain and chronic pain due to osteoarthritis.

Studies in Chronic Low Back Pain —

The efficacy of Cymbalta in chronic low back pain (CLBP) was assessed in two double-blind, placebo-controlled, randomized clinical trials of 13-weeks duration (Study CLBP-1 and Study CLBP-2), and one of 12-weeks duration (CLBP-3). CLBP-1 and CLBP-3 demonstrated efficacy of Cymbalta in the treatment of chronic low back pain. Patients in all studies had no signs of radiculopathy or spinal stenosis.

Study CLBP-1: Two hundred thirty-six adult patients (N=115 on Cymbalta, N=121 on placebo) enrolled and 182 (77%) completed 13-week treatment phase. After 7 weeks of treatment, Cymbalta patients with less than 30% reduction in average daily pain and who were able to tolerate duloxetine 60 mg once daily had their dose of Cymbalta, in a double-blinded fashion, increased to 120 mg once daily for the remainder of the study. Patients had a mean baseline pain rating of 6 on a numerical rating scale ranging from 0 (no pain) to 10 (worst possible pain). After 13 weeks of treatment, patients taking Cymbalta 60-120 mg daily had a significantly greater pain reduction compared to placebo. Randomization was stratified by the patients' baseline NSAIDs-use status. Subgroup analyses did not indicate that there were differences in treatment outcomes as a function of NSAIDs use.

Study CLBP-2: Four hundred and four patients were randomized to receive fixed doses of Cymbalta daily or a matching placebo (N=59 on Cymbalta 20 mg, N=116 on Cymbalta 60 mg, N=112 on Cymbalta 120 mg, N=117 on placebo) and 267 (66%) completed the entire 13-week study. After 13 weeks of treatment, none of the three Cymbalta doses showed a statistically significant difference in pain reduction compared to placebo.

Study CLBP-3: Four hundred and one patients were randomized to receive fixed doses of Cymbalta 60 mg daily or placebo (N=198 on Cymbalta, N=203 on placebo), and 303 (76%) completed the study. Patients had a mean baseline pain rating of 6 on a numerical rating scale ranging from 0 (no pain) to 10 (worst possible pain). After 12 weeks of treatment, patients taking Cymbalta 60 mg daily had significantly greater pain reduction compared to placebo.

For various degrees of improvement in pain from baseline to study endpoint, Figures 5 and 6 show the fraction of patients in CLBP-1 and CLBP-3 achieving that degree of improvement. The figures are cumulative, so that patients whose change from baseline is, for example, 50%, are also included at every level of improvement below 50%. Patients who did not complete the study were assigned the value of 0% improvement.

Figure 5: Percentage of Patients Achieving Various Levels of Pain Relief as Measured by 24-Hour Average Pain Severity – CLBP-1
Figure 6: Percentage of Patients Achieving Various Levels of Pain Relief as Measured by 24-Hour Average Pain Severity – CLBP-3

Studies in Chronic Pain Due to Osteoarthritis —

The efficacy of Cymbalta in chronic pain due to osteoarthritis was assessed in 2 double-blind, placebo-controlled, randomized clinical trials of 13-weeks duration (Study OA-1 and Study OA-2). All patients in both studies fulfilled the ACR clinical and radiographic criteria for classification of idiopathic osteoarthritis of the knee. Randomization was stratified by the patients' baseline NSAIDs-use status. Patients assigned to Cymbalta started treatment in both studies at a dose of 30 mg once daily for one week. After the first week, the dose of Cymbalta was increased to 60 mg once daily. After 7 weeks of treatment with Cymbalta 60 mg once daily, in OA-1 patients with sub-optimal response to treatment (<30% pain reduction) and tolerated duloxetine 60 mg once daily had their dose increased to 120 mg. However, in OA-2, all patients, regardless of their response to treatment after 7 weeks, were re-randomized to either continue receiving Cymbalta 60 mg once daily or have their dose increased to 120 mg once daily for the remainder of the study. Patients in the placebo treatment groups in both studies received a matching placebo for the entire duration of studies. For both studies, efficacy analyses were conducted using 13-week data from the combined Cymbalta 60 mg and 120 mg once daily treatment groups compared to the placebo group.

Study OA-1: Two hundred fifty-six patients (N=128 on Cymbalta, N=128 on placebo) enrolled and 204 (80%) completed the study. Patients had a mean baseline pain rating of 6 on a numerical rating scale ranging from 0 (no pain) to 10 (worst possible pain). After 13 weeks of treatment, patients taking Cymbalta had significantly greater pain reduction. Subgroup analyses did not indicate that there were differences in treatment outcomes as a function of NSAIDs use.

Study OA-2: Two hundred thirty-one patients (N=111 on Cymbalta, N=120 on placebo) enrolled and 173 (75%) completed the study. Patients had a mean baseline pain of 6 on a numerical rating scale ranging from 0 (no pain) to 10 (worst possible pain). After 13 weeks of treatment, patients taking Cymbalta did not show a significantly greater pain reduction.

In Study OA-1, for various degrees of improvement in pain from baseline to study endpoint, Figure 7 shows the fraction of patients achieving that degree of improvement. The figure is cumulative, so that patients whose change from baseline is, for example, 50%, are also included at every level of improvement below 50%. Patients who did not complete the study were assigned the value of 0% improvement.

Figure 7: Percentage of Patients Achieving Various Levels of Pain Relief as Measured by 24-Hour Average Pain Severity – OA-1

16 HOW SUPPLIED/STORAGE AND HANDLING

Repackaged by Aphena Pharma Solutions - TN.
See Repackaging Information for available configurations.

16.1 How Supplied

Cymbalta is available as delayed release capsules in the following strengths, colors, imprints, and presentations:

Features | Strengths
 | 20 mga | 30 mga | 60 mga
Body color | Opaque green | Opaque white | Opaque green
Cap color | Opaque green | Opaque blue | Opaque blue
Cap imprint | Lilly 3235 | Lilly 3240 | Lilly 3270
Body imprint | 20mg | 30mg | 60mg
Capsule number | PU3235 | PU3240 | PU3270
Presentations and NDC Codes
Bottles of 30 | NA | 0002-3240-30 | 0002-3270-30
Bottles of 60 | 0002-3235-60 | NA | NA
Bottles of 90 | NA | 0002-3240-90 | NA
Bottles of 1000 | NA | NA | 0002-3270-04
Blisters ID†100 | NA | 0002-3240-33 | 0002-3270-33
a equivalent to duloxetine base
† Identi-Dose® (unit dose medication, Lilly)

16.2 Storage and Handling

Store at 25°C (77°F); excursions permitted to 15-30°C (59-86°F) [see USP Controlled Room Temperature].

17 PATIENT COUNSELING INFORMATION

See FDA-approved patient labeling (Medication Guide).

17.1 Information on Medication Guide

Prescribers or other health professionals should inform patients, their families, and their caregivers about the benefits and risks associated with treatment with Cymbalta and should counsel them in its appropriate use. A patient Medication Guide is available for Cymbalta. The prescriber or health professional should instruct patients, their families, and their caregivers to read the Medication Guide before starting Cymbalta and each time their prescription is renewed, and should assist them in understanding its contents. Patients should be given the opportunity to discuss the contents of the Medication Guide and to obtain answers to any questions they may have. The complete text of the Medication Guide is reprinted at the end of this document.

Patients should be advised of the following issues and asked to alert their prescriber if these occur while taking Cymbalta.

17.2 Suicidal Thoughts and Behaviors

Patients, their families, and their caregivers should be encouraged to be alert to the emergence of anxiety, agitation, panic attacks, insomnia, irritability, hostility, aggressiveness, impulsivity, akathisia (psychomotor restlessness), hypomania, mania, other unusual changes in behavior, worsening of depression, and suicidal ideation, especially early during antidepressant treatment and when the dose is adjusted up or down. Families and caregivers of patients should be advised to observe for the emergence of such symptoms on a day-to-day basis, since changes may be abrupt. Such symptoms should be reported to the patient's prescriber or health professional, especially if they are severe, abrupt in onset, or were not part of the patient's presenting symptoms. Symptoms such as these may be associated with an increased risk for suicidal thinking and behavior and indicate a need for very close monitoring and possibly changes in the medication [see Boxed Warning, and Warnings and Precautions (5.1)].

17.3 Medication Administration

Cymbalta should be swallowed whole and should not be chewed or crushed, nor should the capsule be opened and its contents be sprinkled on food or mixed with liquids. All of these might affect the enteric coating.

17.4 Continuing the Therapy Prescribed

While patients may notice improvement with Cymbalta therapy in 1 to 4 weeks, they should be advised to continue therapy as directed.

17.5 Hepatotoxicity

Patients should be informed that severe liver problems, sometimes fatal, have been reported in patients treated with Cymbalta. Patients should be instructed to talk to their healthcare provider if they develop itching, right upper belly pain, dark urine, or yellow skin/eyes while taking Cymbalta, which may be signs of liver problems. Patients should talk to their healthcare provider about their alcohol consumption. Use of Cymbalta with heavy alcohol intake may be associated with severe liver injury [see Warnings and Precautions (5.2)].

17.6 Alcohol

Although Cymbalta does not increase the impairment of mental and motor skills caused by alcohol, use of Cymbalta concomitantly with heavy alcohol intake may be associated with severe liver injury. For this reason, Cymbalta should not be prescribed for patients with substantial alcohol use [see Warnings and Precautions (5.2) and Drug Interactions (7.15)].

17.7 Orthostatic Hypotension and Syncope

Patients should be advised of the risk of orthostatic hypotension and syncope, especially during the period of initial use and subsequent dose escalation, and in association with the use of concomitant drugs that might potentiate the orthostatic effect of duloxetine [see Warnings and Precautions (5.3)].

17.8 Serotonin Syndrome

Patients should be cautioned about the risk of serotonin syndrome with the concomitant use of Cymbalta and other serotonergic agents including triptans, tricyclic antidepressants, fentanyl, lithium, tramadol, buspirone, tryptophan and St. John's Wort [see Contraindications (4.1), Warnings and Precautions (5.4), and Drug Interactions (7.14)].

Patients should be advised of the signs and symptoms associated with serotonin syndrome that may include mental status changes (e.g., agitation, hallucinations, delirium, and coma), autonomic instability (e.g., tachycardia, labile blood pressure, dizziness, diaphoresis, flushing, hyperthermia), neuromuscular changes (e.g., tremor, rigidity, myoclonus, hyperreflexia, incoordination), seizures, and/or gastrointestinal symptoms (e.g., nausea, vomiting, diarrhea). Patients should be cautioned to seek medical care immediately if they experience these symptoms.

17.9 Abnormal Bleeding

Patients should be cautioned about the concomitant use of duloxetine and NSAIDs, aspirin, warfarin, or other drugs that affect coagulation since combined use of psychotropic drugs that interfere with serotonin reuptake and these agents has been associated with an increased risk of bleeding [see Warnings and Precautions (5.5)].

17.10 Severe Skin Reactions

Patients should be cautioned that Cymbalta may cause serious skin reactions. This may need to be treated in a hospital and may be life-threatening. Patients should be counseled to call their doctor right away or get emergency help if they have skin blisters, peeling rash, sores in their mouth, hives, or any other allergic reactions [see Warnings and Precautions (5.6)].

17.11 Discontinuation of Treatment

Patients should be instructed that discontinuation of Cymbalta may be associated with symptoms such as dizziness, headache, nausea, diarrhea, paresthesia, irritability, vomiting, insomnia, anxiety, hyperhidrosis, and fatigue, and should be advised not to alter their dosing regimen, or stop taking Cymbalta without consulting their physician [see Warnings and Precautions (5.7)].

17.12 Activation of Mania or Hypomania

Patients with depressive symptoms should be adequately screened for risk of bipolar disorder (e.g. family history of suicide, bipolar disorder, and depression) prior to initiating treatment with Cymbalta. Patients should be advised to report any signs or symptoms of a manic reaction such as greatly increased energy, severe trouble sleeping, racing thoughts, reckless behavior, talking more or faster than usual, unusually grand ideas, and excessive happiness or irritability [see Warnings and Precautions (5.8)].

17.13 Seizures

Patients should be advised to inform their physician if they have a history of seizure disorder [see Warnings and Precautions (5.9)].

17.14 Effects on Blood Pressure

Patients should be cautioned that Cymbalta may cause an increase in blood pressure [see Warnings and Precautions (5.10)].

17.15 Concomitant Medications

Patients should be advised to inform their physicians if they are taking, or plan to take, any prescription or over-the-counter medications, since there is a potential for interactions [see Dosage and Administration (2.5), Contraindications (4.1), Warnings and Precautions (5.4 and 5.11), and Drug Interactions (7)].

17.16 Hyponatremia

Patients should be advised that hyponatremia has been reported as a result of treatment with SNRIs and SSRIs, including Cymbalta. Patients should be advised of the signs and symptoms of hyponatremia [see Warnings and Precautions (5.12)].

17.17 Concomitant Illnesses

Patients should be advised to inform their physicians about all of their medical conditions [see Warnings and Precautions (5.13)].

17.18 Urinary Hesitancy and Retention

Cymbalta is in a class of medicines that may affect urination. Patients should be instructed to consult with their healthcare provider if they develop any problems with urine flow [see Warnings and Precautions (5.14)].

17.19 Pregnancy and Breast Feeding

Patients should be advised to notify their physician if they

- become pregnant during therapy
- intend to become pregnant during therapy
- are breast feeding [see Dosage and Administration (2.3) and Use in Specific Populations (8.1, 8.2, and 8.3)].

Lilly maintains a pregnancy registry to monitor the pregnancy outcomes of women exposed to Cymbalta while pregnant. Healthcare providers are encouraged to register any patient who is exposed to Cymbalta during pregnancy by calling the Cymbalta Pregnancy Registry at 1-866-814-6975 or by visiting www.cymbaltapregnancyregistry.com.

17.20 Interference with Psychomotor Performance

Any psychoactive drug may impair judgment, thinking, or motor skills. Although in controlled studies Cymbalta has not been shown to impair psychomotor performance, cognitive function, or memory, it may be associated with sedation and dizziness. Therefore, patients should be cautioned about operating hazardous machinery including automobiles, until they are reasonably certain that Cymbalta therapy does not affect their ability to engage in such activities.

Literature revised November 9, 2012

Marketed by: Lilly USA, LLC, Indianapolis, IN 46285, USA

Copyright © 2004, 2012, Eli Lilly and Company. All rights reserved.

PV 9474 AMP

Medication Guide

Cymbalta® [sim-BALL-tah]
(Duloxetine Delayed-Release Capsules)

Read the Medication Guide that comes with Cymbalta® before you start taking it and each time you get a refill. There may be new information. This Medication Guide does not take the place of talking to your healthcare provider about your medical condition or treatment. Talk with your healthcare provider if there is something you do not understand or want to learn more about.

What is the most important information I should know about Cymbalta?

Cymbalta and other antidepressant medicines may cause serious side effects, including:

1. Suicidal thoughts or actions:

- Cymbalta and other antidepressant medicines may increase suicidal thoughts or actions in some children, teenagers, or young adults within the first few months of treatment or when the dose is changed.
- Depression or other serious mental illnesses are the most important causes of suicidal thoughts or actions.
- Watch for these changes and call your healthcare provider right away if you notice:
  - New or sudden changes in mood, behavior, actions, thoughts, or feelings, especially if severe.
  - Pay particular attention to such changes when Cymbalta is started or when the dose is changed.
  - Keep all follow-up visits with your healthcare provider and call between visits if you are worried about symptoms.

Call your healthcare provider right away if you have any of the following symptoms, or call 911 if an emergency, especially if they are new, worse, or worry you:

- attempts to commit suicide
- acting on dangerous impulses
- acting aggressive or violent
- thoughts about suicide or dying
- new or worse depression
- new or worse anxiety or panic attacks
- feeling agitated, restless, angry or irritable
- trouble sleeping
- an increase in activity or talking more than what is normal for you
- other unusual changes in behavior or mood

Call your healthcare provider right away if you have any of the following symptoms, or call 911 if an emergency. Cymbalta may be associated with these serious side effects:

2. Liver damage- symptoms may include:

- itching
- right upper abdominal pain
- dark urine
- hepatitis with yellow skin or eyes
- enlarged liver
- increased liver enzymes

3. Serotonin Syndrome - This condition can be life-threatening and may include:

- agitation, hallucinations, coma or other changes in mental status
- coordination problems or muscle twitching (overactive reflexes)
- racing heartbeat, high or low blood pressure
- sweating or fever
- nausea, vomiting, or diarrhea
- muscle rigidity
- dizziness
- flushing
- tremor
- seizures

4. Abnormal bleeding: Cymbalta and other antidepressant medicines may increase your risk of bleeding or bruising, especially if you take the blood thinner warfarin (Coumadin*, Jantoven*), a non-steroidal anti-inflammatory drug (NSAIDs, like ibuprofen or naproxen), or aspirin.

5. Severe skin reactions: Cymbalta may cause serious skin reactions that may require stopping its use. This may need to be treated in a hospital and may be life-threatening. Call your doctor right away or get emergency help if you have skin blisters, peeling rash, sores in the mouth, hives or any other allergic reactions.

6. Manic episodes:

- greatly increased energy
- severe trouble sleeping
- racing thoughts
- reckless behavior
- unusually grand ideas
- excessive happiness or irritability
- talking more or faster than usual

7. Seizures or convulsions

8. Changes in blood pressure. Monitor your blood pressure before starting and throughout treatment. Cymbalta may:

- increase your blood pressure.
- decrease your blood pressure when standing and cause dizziness or fainting, mostly when first starting Cymbalta or when increasing the dose.

9. Low salt (sodium) levels in the blood. Elderly people may be at greater risk for this. Symptoms may include:

- headache
- weakness or feeling unsteady
- confusion, problems concentrating or thinking or memory problems

10. Problems with urination include:

- decreased urine flow
- unable to pass any urine

11. Changes in appetite or weight. Children and adolescents should have height and weight monitored during treatment.

Do not stop Cymbalta without first talking to your healthcare provider. Stopping Cymbalta too quickly or changing from another antidepressant too quickly may result in serious symptoms including:

- anxiety, irritability
- feeling tired or problems sleeping
- headache, sweating, dizziness
- electric shock-like sensations
- vomiting, nausea, diarrhea

What is Cymbalta?

Cymbalta is a prescription medicine used to treat depression. It is important to talk with your healthcare provider about the risks of treating depression and also the risks of not treating it. You should discuss all treatment choices with your healthcare provider.

Cymbalta is also used to treat or manage:

- Major Depressive Disorder (MDD)
- Generalized Anxiety Disorder (GAD)
- Diabetic Peripheral Neuropathic Pain (DPNP)
- Fibromyalgia (FM)
- Chronic Musculoskeletal Pain

Talk to your healthcare provider if you do not think that your condition is getting better with Cymbalta treatment.

Who should not take Cymbalta?

Do NOT take Cymbalta if you:

- have uncontrolled narrow-angle glaucoma
- take a Monoamine Oxidase Inhibitor (MAOI). Ask your healthcare provider or pharmacist if you are not sure if you take an MAOI, including the antibiotic linezolid.
- Do not take an MAOI within 5 days of stopping Cymbalta unless directed to do so by your physician.
- Do not start Cymbalta if you stopped taking an MAOI in the last 2 weeks unless directed to do so by your physician.

People who take Cymbalta close in time to an MAOI may have serious or even life-threatening side effects. Get medical help right away if you have any of these symptoms:

- high fever
- uncontrolled muscle spasms
- stiff muscles
- rapid changes in heart rate or blood pressure
- confusion
- loss of consciousness (pass out)
- take Mellaril* (thioridazine) because this can cause serious heart rhythm problems or sudden death

What should I tell my healthcare provider before taking Cymbalta? Ask if you are not sure.

Before starting Cymbalta, tell your healthcare provider if you:

- Are taking certain drugs such as:
  - Triptans used to treat migraine headache
  - Medicines used to treat mood, anxiety, psychotic or thought disorders, including tricyclics, lithium, buspirone, SSRIs, SNRIs or MAOIs
  - Tramadol and fentanyl
  - Cimetidine
  - The antibiotics ciprofloxacin, enoxacin
  - Medicine to control heart rate such as propafenone, flecainide, quinidine
  - Theophylline
  - The blood thinner warfarin (Coumadin*, Jantoven*)
  - Non-steroidal anti-inflammatory drug (NSAID), like ibuprofen, naproxen or aspirin.
  - Over-the-counter supplements such as tryptophan or St. John's Wort
- have heart problems or high blood pressure
- have diabetes (Cymbalta treatment worsens the control of blood sugar in some patients with diabetes)
- have liver problems
- have kidney problems
- have glaucoma
- have or had seizures or convulsions
- have bipolar disorder or mania
- have low sodium levels in your blood
- have delayed stomach emptying
- have or had bleeding problems
- are pregnant or plan to become pregnant. It is not known if Cymbalta will harm your unborn baby. Talk to your healthcare provider about the benefits and risks of treating depression or other conditions with Cymbalta during pregnancy. Lilly, the company that markets Cymbalta, maintains a pregnancy registry. The Cymbalta Pregnancy Registry collects information from voluntary participants who are pregnant and who have been exposed to Cymbalta at any time during pregnancy. Women who are interested in enrolling may contact the Registry directly by calling 1-866-814-6975 or by visiting www.cymbaltapregnancyregistry.com
- are breast-feeding or plan to breast-feed. Some Cymbalta may pass into your breast milk. Talk to your healthcare provider about the best way to feed your baby while taking Cymbalta.

Tell your healthcare provider about all the medicines that you take, including prescription and non-prescription medicines, vitamins, and herbal supplements. Cymbalta and some medicines may interact with each other, may not work as well, or may cause serious side effects.

Your healthcare provider or pharmacist can tell you if it is safe to take Cymbalta with your other medicines. Do not start or stop any medicine while taking Cymbalta without talking to your healthcare provider first.

If you take Cymbalta, you should not take any other medicines that contain duloxetine.

How should I take Cymbalta?

- Take Cymbalta exactly as prescribed. Your healthcare provider may need to change the dose of Cymbalta until it is the right dose for you.
- Do not open, break or chew the capsule; it must be swallowed whole.
- Cymbalta may be taken with or without food.
- If you miss a dose of Cymbalta, take the missed dose as soon as you remember. If it is almost time for the next dose, skip the missed dose and take your next dose at the regular time. Do not take two doses of Cymbalta at the same time.
- If you take too much Cymbalta, call your healthcare provider or poison control center right away, or get emergency treatment.
- When switching from another antidepressant to Cymbalta your doctor may want to lower the dose of the initial antidepressant first to potentially avoid side effects.

What should I avoid while taking Cymbalta?

- Cymbalta can cause sleepiness or may affect your ability to make decisions, think clearly, or react quickly. You should not drive, operate heavy machinery, or do other dangerous activities until you know how Cymbalta affects you.
- Use of Cymbalta concomitantly with heavy alcohol intake may be associated with severe liver injury. Avoid heavy alcohol use while taking Cymbalta.

What are the possible side effects of Cymbalta?

Cymbalta may cause serious side effects, including all of those described in the section entitled “What is the most important information I should know about Cymbalta?”

Common possible side effects in people who take Cymbalta include:

- nausea
- dry mouth
- sleepiness
- fatigue
- loss of appetite
- increased sweating
- dizziness

Tell your healthcare provider if you have any side effect that bothers you or that does not go away. These are not all the possible side effects of Cymbalta. For more information, ask your healthcare provider or pharmacist.

CALL YOUR DOCTOR FOR MEDICAL ADVICE ABOUT SIDE EFFECTS. YOU MAY REPORT SIDE EFFECTS TO THE FDA AT 1-800-FDA-1088.

How should I store Cymbalta?

Store Cymbalta at room temperature between 59°F and 86°F (15°C to 30°C).

Keep Cymbalta and all medicines out of the reach of children.

General information about Cymbalta

Medicines are sometimes prescribed for purposes other than those listed in a Medication Guide. Do not use Cymbalta for a condition for which it was not prescribed. Do not give Cymbalta to other people, even if they have the same condition. It may harm them.

This Medication Guide summarizes the most important information about Cymbalta. If you would like more information, talk with your healthcare provider. You may ask your healthcare provider or pharmacist for information about Cymbalta that is written for healthcare professionals.

For more information about Cymbalta call 1-800-Lilly Rx (1-800-545-5979) or go to www. Cymbalta.com.

What are the ingredients in Cymbalta?

Active ingredient: duloxetine hydrochloride

Inactive ingredients:

- Delayed Release Capsules: FD&C Blue No. 2, gelatin, hypromellose, hydroxypropyl methylcellulose acetate succinate, sodium lauryl sulfate, sucrose, sugar spheres, talc, titanium dioxide, and triethyl citrate. The 20 and 60 mg capsules also contain iron oxide yellow.

This Medication Guide has been approved by the U.S. Food and Drug Administration

*The brands listed are trademarks of their respective owners and not trademarks of Eli Lilly and Company.

Medication Guide revised: November 9, 2012

Marketed by: Lilly USA, LLC
Indianapolis, IN 46285, USA

www.cymbalta.com

Cymbalta is a registered trademark of Eli Lilly and Company.

Copyright © 2009, 2012, Eli Lilly and Company. All rights reserved.

PV 7094 AMP

Repackaging Information

Please reference the How Supplied section listed above for a description of individual tablets or capsules. This drug product has been received by Aphena Pharma - TN in a manufacturer or distributor packaged configuration and repackaged in full compliance with all applicable cGMP regulations. The package configurations available from Aphena are listed below:

Count | 30mg
3060 | 43353-303-19

Store between 20°-25°C (68°-77°F). See USP Controlled Room Temperature. Dispense in a tight light-resistant container as defined by USP. Keep this and all drugs out of the reach of children.

Repackaged by:
Cookeville, TN 38506
20140424SC

PRINCIPAL DISPLAY PANEL - 30mg

NDC 43353-303 - Duloxetine HCI (Cymbalta®) DR 30mg - Rx Only